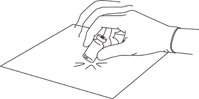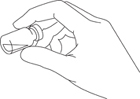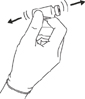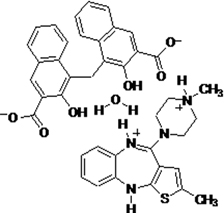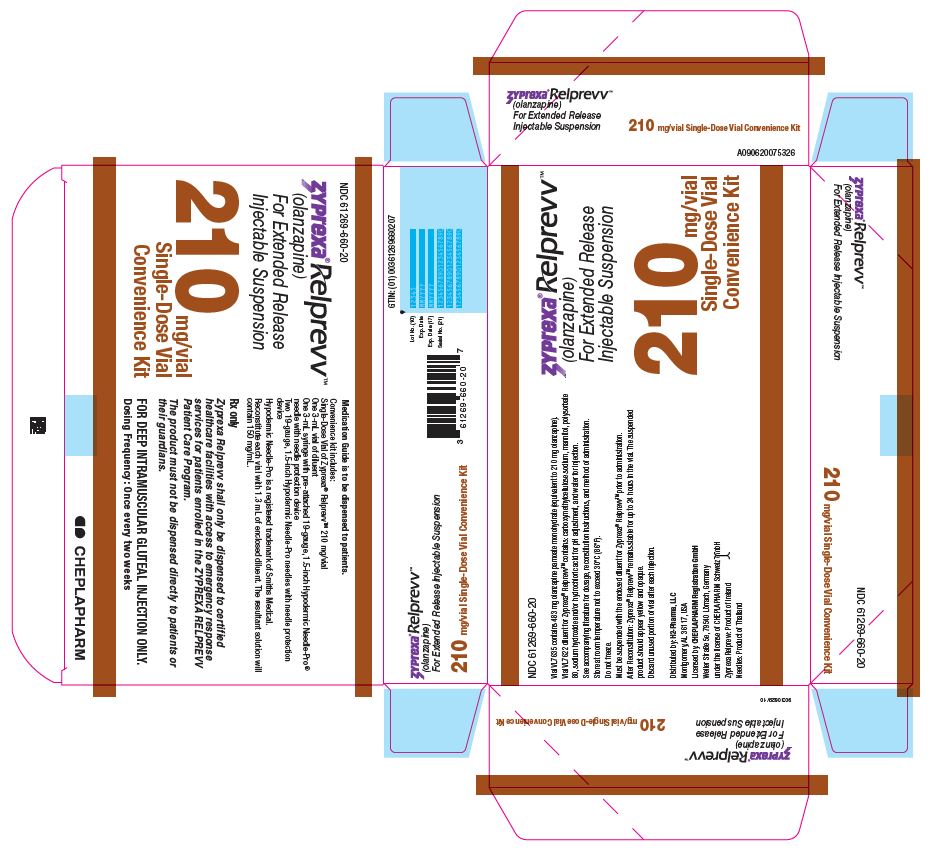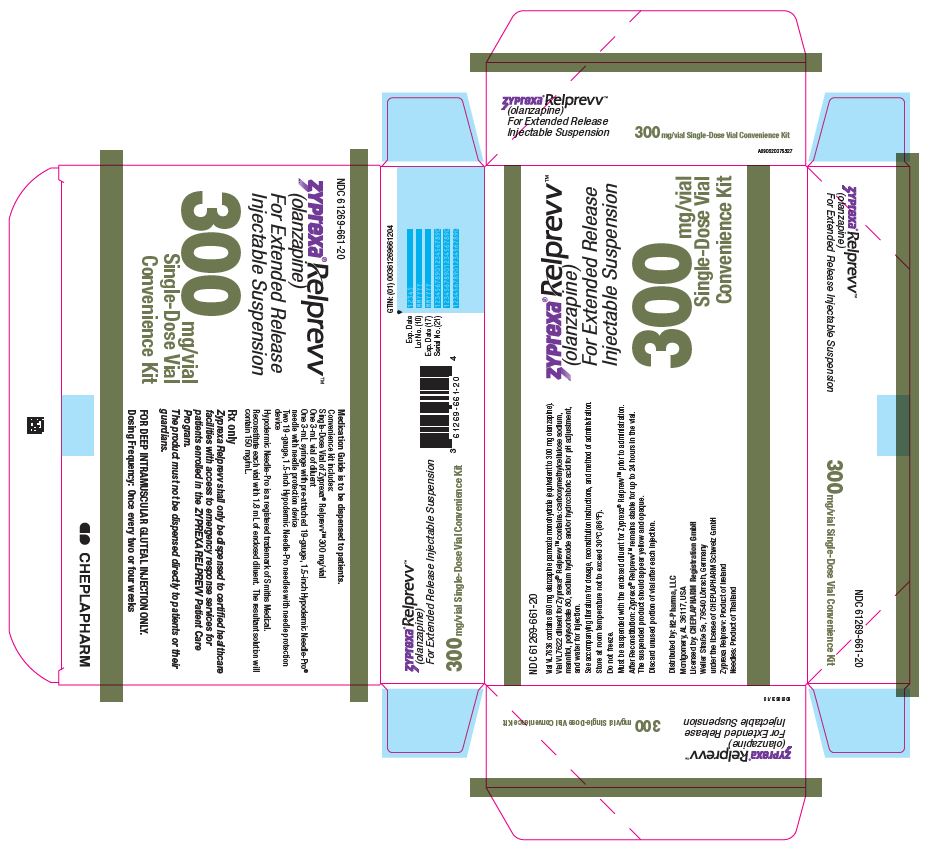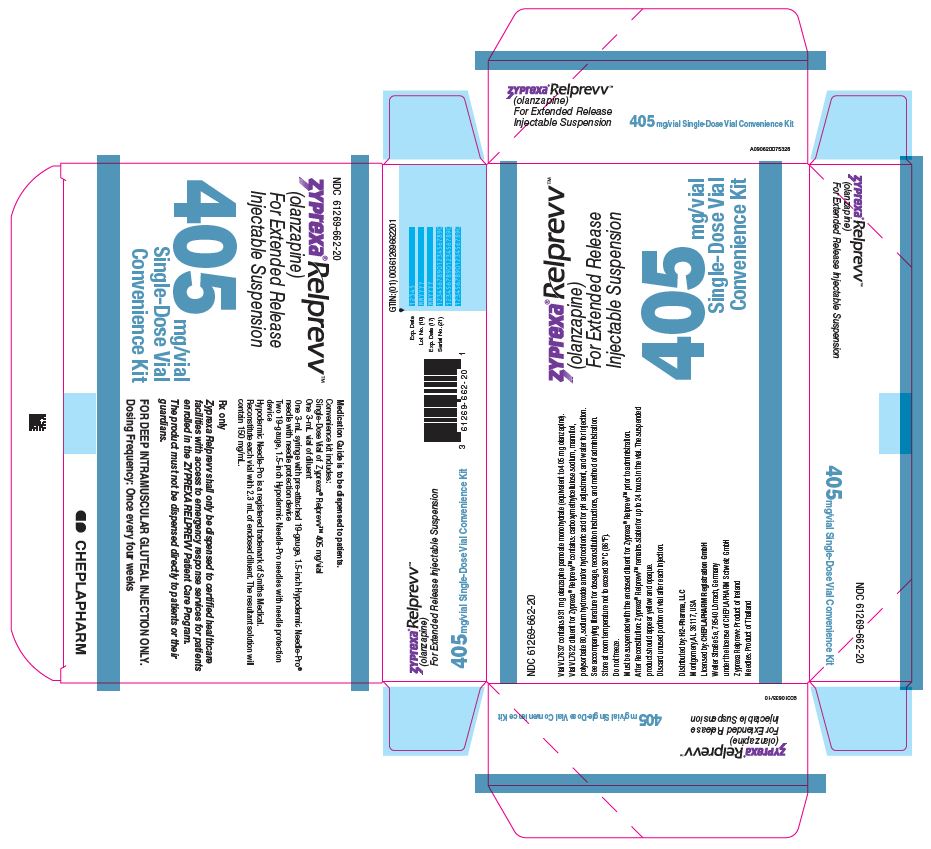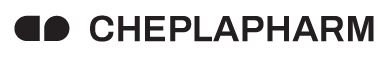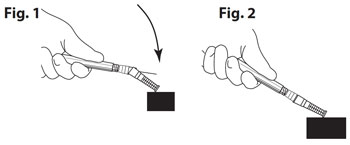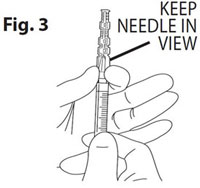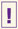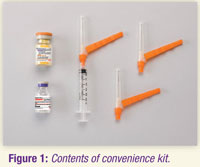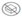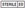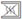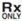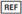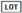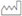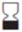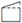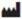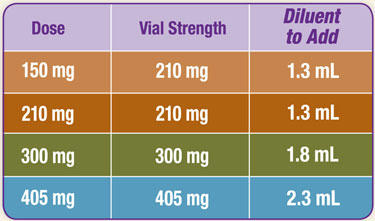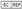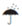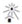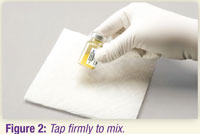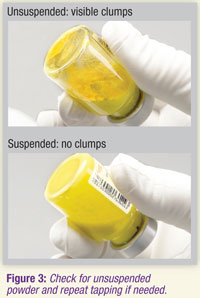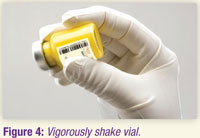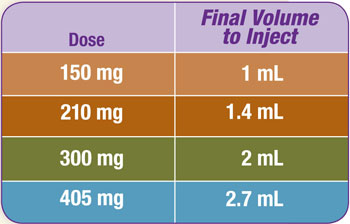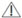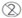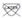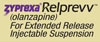 DRUG LABEL: ZYPREXA
NDC: 61269-660 | Form: KIT | Route: INTRAMUSCULAR
Manufacturer: H2-Pharma LLC
Category: prescription | Type: HUMAN PRESCRIPTION DRUG LABEL
Date: 20260211

ACTIVE INGREDIENTS: Olanzapine pamoate 210 mg/1.4 mL
INACTIVE INGREDIENTS: Carboxymethylcellulose sodium, Unspecified 7.5 mg/1 mL; Mannitol 50 mg/1 mL; Polysorbate 80 1.0 mg/1 mL; Hydrochloric acid; Sodium hydroxide; Water

HIGHLIGHTS OF PRESCRIBING INFORMATION

These highlights do not include all the information needed to use ZYPREXA RELPREVV safely and effectively. See full prescribing information for ZYPREXA RELPREVV.
ZYPREXA RELPREVV (olanzapine) For Extended Release Injectable Suspension
Initial U.S. Approval: 1996

RECENT MAJOR CHANGES

None

WARNING: POST-INJECTION DELIRIUM/SEDATION SYNDROME and INCREASED MORTALITY IN ELDERLY PATIENTS WITH DEMENTIA-RELATED PSYCHOSIS

See full prescribing information for complete boxed warning.

- Patients are at risk for severe sedation (including coma) and/or delirium after each injection and must be observed for at least 3 hours in a registered facility with ready access to emergency response services. Because of this risk, ZYPREXA RELPREVV is available only through a restricted distribution program called ZYPREXA RELPREVV Patient Care Program and requires prescriber, healthcare facility, patient, and pharmacy enrollment. (2.1, 5.1, 5.2, 10.2, 17)
- Elderly patients with dementia-related psychosis treated with antipsychotic drugs are at an increased risk of death. ZYPREXA RELPREVV is not approved for the treatment of patients with dementia-related psychosis. (5.3, 8.5, 17)

1 INDICATIONS AND USAGE

ZYPREXA® RELPREVV™ is a long-acting atypical antipsychotic for intramuscular injection indicated for the treatment of schizophrenia. (1.1)

Efficacy was established in two clinical trials in patients with schizophrenia: one 8-week trial in adults and one maintenance trial in adults. (14.1)

2 DOSAGE AND ADMINISTRATION

150 mg/2 wks, 300 mg/4 wks, 210 mg/2 wks, 405 mg/4 wks, or 300 mg/2 wks. See Table 1 for dosing recommendations. (2.1)

ZYPREXA RELPREVV is intended for deep intramuscular gluteal injection only.

- Do not administer intravenously or subcutaneously. (2.1)
- Be aware that there are two ZYPREXA intramuscular formulations with different dosing schedules. ZYPREXA IntraMuscular (10 mg/vial) is a short-acting formulation and should not be confused with ZYPREXA RELPREVV. (2.1)
- Establish tolerability with oral olanzapine prior to initiating treatment. (2.1)
- ZYPREXA RELPREVV doses above 405 mg every 4 weeks or 300 mg every 2 weeks have not been evaluated in clinical trials. (2.1)
- Use in specific populations (including renal and hepatic impaired, and pediatric population) has not been studied. (2.1)
- Must be suspended using only the diluent for ZYPREXA RELPREVV provided in the convenience kit. (2.2)

3 DOSAGE FORMS AND STRENGTHS

Powder for suspension for single-dose intramuscular use only: 210 mg/vial, 300 mg/vial, and 405 mg/vial. (3, 11, 16)

4 CONTRAINDICATIONS

None.

5 WARNINGS AND PRECAUTIONS

- Elderly Patients with Dementia-Related Psychosis: Increased risk of death and increased incidence of cerebrovascular adverse events (e.g. stroke, transient ischemic attack). (5.3)
- Suicide: The possibility of a suicide attempt is inherent in schizophrenia, and close supervision of high-risk patients should accompany drug therapy. (5.4)
- Neuroleptic Malignant Syndrome: Manage with immediate discontinuation and close monitoring. (5.5)
- Drug Reaction with Eosinophilia and Systemic Symptoms (DRESS): Discontinue if DRESS is suspected. (5.6)
- Metabolic Changes: Atypical antipsychotic drugs have been associated with metabolic changes including hyperglycemia, dyslipidemia, and weight gain. (5.7)
  - Hyperglycemia and Diabetes Mellitus: In some cases extreme and associated with ketoacidosis or hyperosmolar coma or death, has been reported in patients taking olanzapine. Patients taking olanzapine should be monitored for symptoms of hyperglycemia and undergo fasting blood glucose testing at the beginning of, and periodically during, treatment. (5.7)
  - Dyslipidemia: Undesirable alterations in lipids have been observed. Appropriate clinical monitoring is recommended, including fasting blood lipid testing at the beginning of, and periodically during, treatment. (5.7)
  - Weight Gain: Potential consequences of weight gain should be considered. Patients should receive regular monitoring of weight. (5.7)
- Tardive Dyskinesia: Discontinue if clinically appropriate. (5.8)
- Orthostatic Hypotension: Orthostatic hypotension associated with dizziness, tachycardia, bradycardia and, in some patients, syncope, may occur especially during initial dose titration. Use caution in patients with cardiovascular disease, cerebrovascular disease, and those conditions that could affect hemodynamic responses. (5.9)
- Leukopenia, Neutropenia, and Agranulocytosis: Has been reported with antipsychotics, including ZYPREXA. Patients with a history of a clinically significant low white blood cell count (WBC) or drug induced leukopenia/neutropenia should have their complete blood count (CBC) monitored frequently during the first few months of therapy and discontinuation of ZYPREXA RELPREVV should be considered at the first sign of a clinically significant decline in WBC in the absence of other causative factors. (5.11)
- Seizures: Use cautiously in patients with a history of seizures or with conditions that potentially lower the seizure threshold. (5.13)
- Anticholinergic (antimuscarinic) Effects: Use with caution with other anticholinergic drugs and in patients with urinary retention, prostatic hypertrophy, constipation, paralytic ileus or related conditions. (5.16, 7.1)
- Potential for Cognitive and Motor Impairment: Has potential to impair judgment, thinking, and motor skills. Use caution when operating machinery. (5.14)
- Hyperprolactinemia: May elevate prolactin levels. (5.17)
- Laboratory Tests: Monitor fasting blood glucose and lipid profiles at the beginning of, and periodically during, treatment. (5.18)

6 ADVERSE REACTIONS

Most common adverse reactions (≥5% in at least one of the treatment groups and greater than placebo) associated with ZYPREXA RELPREVV treatment: headache, sedation, weight gain, cough, diarrhea, back pain, nausea, somnolence, dry mouth, nasopharyngitis, increased appetite, and vomiting. (6.1)

To report SUSPECTED ADVERSE REACTIONS, contact the Safety Call Center at 1-866-770-9010 or FDA at 1-800-FDA-1088 or www.fda.gov/medwatch

7 DRUG INTERACTIONS

- CNS Acting Drugs: Caution should be used when used in combination with other centrally acting drugs and alcohol. (7.2)
- Antihypertensive Agents: Enhanced antihypertensive effect. (7.2)
- Levodopa and Dopamine Agonists: May antagonize levodopa/dopamine agonists. (7.2)
- Diazepam: May potentiate orthostatic hypotension. (7.1, 7.2)
- Alcohol: May potentiate orthostatic hypotension. (7.1)
- Carbamazepine: Increased clearance of olanzapine. (7.1)
- Fluvoxamine: May increase olanzapine levels. (7.1)

8 USE IN SPECIFIC POPULATIONS

- Pregnancy: May cause extrapyramidal and/or withdrawal symptoms in neonates with third trimester exposure. (8.1)
- Pediatric Use: Safety and effectiveness of ZYPREXA RELPREVV in children <18 years of age have not been established. (8.4)

FULL PRESCRIBING INFORMATION

WARNING: POST-INJECTION DELIRIUM/SEDATION SYNDROME and INCREASED MORTALITY IN ELDERLY PATIENTS WITH DEMENTIA-RELATED PSYCHOSIS

Post-Injection Delirium/Sedation Syndrome— Adverse events with signs and symptoms consistent with olanzapine overdose, in particular, sedation (including coma) and/or delirium, have been reported following injections of ZYPREXA RELPREVV. ZYPREXA RELPREVV must be administered in a registered healthcare facility with ready access to emergency response services. After each injection, patients must be observed at the healthcare facility by a healthcare professional for at least 3 hours. Because of this risk, ZYPREXA RELPREVV is available only through a restricted distribution program called ZYPREXA RELPREVV Patient Care Program and requires prescriber, healthcare facility, patient, and pharmacy enrollment [see Dosage and Administration (2.1), Warnings and Precautions (5.1, 5.2), Overdosage (10.2), and Patient Counseling Information (17)].

Increased Mortality in Elderly Patients with Dementia-Related Psychosis— Elderly patients with dementia-related psychosis treated with antipsychotic drugs are at an increased risk of death. Analyses of seventeen placebo-controlled trials (modal duration of 10 weeks), largely in patients taking atypical antipsychotic drugs, revealed a risk of death in drug-treated patients of between 1.6 to 1.7 times the risk of death in placebo-treated patients. Over the course of a typical 10-week controlled trial, the rate of death in drug-treated patients was about 4.5%, compared to a rate of about 2.6% in the placebo group. Although the causes of death were varied, most of the deaths appeared to be either cardiovascular (e.g., heart failure, sudden death) or infectious (e.g., pneumonia) in nature. Observational studies suggest that, similar to atypical antipsychotic drugs, treatment with conventional antipsychotic drugs may increase mortality. The extent to which the findings of increased mortality in observational studies may be attributed to the antipsychotic drug as opposed to some characteristic(s) of the patients is not clear. ZYPREXA RELPREVV is not approved for the treatment of patients with dementia-related psychosis [see Warnings and Precautions (5.3), Use in Specific Populations (8.5) and Patient Counseling Information (17)].

1 INDICATIONS AND USAGE

ZYPREXA RELPREVV is available only through a restricted distribution program [see Warnings and Precautions (5.2)]. ZYPREXA RELPREVV must not be dispensed directly to a patient. For a patient to receive treatment, the prescriber, healthcare facility, patient, and pharmacy must all be enrolled in the ZYPREXA RELPREVV Patient Care Program. To enroll, call 1-877-772-9390.

1.1 Schizophrenia

ZYPREXA RELPREVV is indicated for the treatment of schizophrenia. Efficacy was established in two clinical trials in patients with schizophrenia: one 8-week trial in adults and one maintenance trial in adults [see Clinical Studies (14.1)].

2 DOSAGE AND ADMINISTRATION

2.1 Dosage

ZYPREXA RELPREVV is intended for deep intramuscular gluteal injection only and should not be administered intravenously or subcutaneously.

Be aware that there are two ZYPREXA intramuscular formulations with different dosing schedules. ZYPREXA IntraMuscular (10 mg/vial) is a short-acting formulation and should not be confused with ZYPREXA RELPREVV. Refer to the package insert for ZYPREXA IntraMuscular for more information about that product.

Establish tolerability with oral olanzapine prior to initiating treatment.

ZYPREXA RELPREVV should be administered by a healthcare professional every 2 to 4 weeks by deep intramuscular gluteal injection using a 19-gauge, 1.5-inch needle. Following insertion of the needle into the muscle, aspiration should be maintained for several seconds to ensure that no blood is drawn into the syringe. If any blood is aspirated into the syringe, it should be discarded and fresh drug should be prepared using a new convenience kit. The injection should be performed at a steady, continuous pressure. Do not massage the injection site.

Dose Selection — The efficacy of ZYPREXA RELPREVV has been demonstrated within the range of 150 mg to 300 mg administered every 2 weeks and with 405 mg administered every 4 weeks. Dose recommendations considering oral ZYPREXA and ZYPREXA RELPREVV are shown in Table 1.

Table 1: Recommended Dosing for ZYPREXA RELPREVV Based on Correspondence to Oral ZYPREXA Doses
Target Oral ZYPREXA Dose | Dosing of ZYPREXA RELPREVV During the First 8 Weeks | Maintenance Dose After 8 Weeks of ZYPREXA RELPREVV Treatment
10 mg/day | 210 mg/2 weeks or | 150 mg/2 weeks or
 | 405 mg/4 weeks | 300 mg/4 weeks
15 mg/day | 300 mg/2 weeks | 210 mg/2 weeks or
 |  | 405 mg/4 weeks
20 mg/day | 300 mg/2 weeks | 300 mg/2 weeks

ZYPREXA RELPREVV doses greater than 405 mg every 4 weeks or 300 mg every 2 weeks have not been evaluated in clinical trials.

Post-Injection Delirium/Sedation Syndrome — During premarketing clinical studies, adverse events that presented with signs and symptoms consistent with olanzapine overdose, in particular, sedation (including coma) and/or delirium, were reported in patients following an injection of ZYPREXA RELPREVV [see Boxed Warning, Warnings and Precautions (5.1), and Overdosage (10.1)]. Patients should be informed of this risk and how to recognize related symptoms [see Patient Counseling Information (17)]. ZYPREXA RELPREVV must be administered in a registered healthcare facility with ready access to emergency response services. After each ZYPREXA RELPREVV injection, a healthcare professional must continuously observe the patient at the healthcare facility for at least 3 hours for symptoms consistent with olanzapine overdose, including sedation (ranging from mild in severity to coma) and/or delirium (including confusion, disorientation, agitation, anxiety, and other cognitive impairment). Other symptoms noted include extrapyramidal symptoms, dysarthria, ataxia, aggression, dizziness, weakness, hypertension, and convulsion. The potential for onset of an event is greatest within the first hour. The majority of cases have occurred within the first 3 hours after injection; however, the event has occurred after 3 hours. Following the 3-hour observation period, healthcare professionals must confirm that the patient is alert, oriented, and absent of any signs and symptoms of post-injection delirium/sedation syndrome prior to being released. All patients must be accompanied to their destination upon leaving the facility. For the remainder of the day of each injection, patients should not drive or operate heavy machinery, and should be advised to be vigilant for symptoms of post-injection delirium/sedation syndrome and be able to obtain medical assistance if needed. If post-injection delirium/sedation syndrome is suspected, close medical supervision and monitoring should be instituted in a facility capable of resuscitation [see Overdosage (10)].

Dosing in Specific Populations — Tolerance of oral ZYPREXA should be established prior to initiating treatment with ZYPREXA RELPREVV. The recommended starting dose is ZYPREXA RELPREVV 150 mg/4 wks in patients who are debilitated, who have a predisposition to hypotensive reactions, who otherwise exhibit a combination of factors that may result in slower metabolism of olanzapine (e.g., nonsmoking female patients ≥65 years of age), or who may be more pharmacodynamically sensitive to olanzapine. When indicated, dose escalation should be undertaken with caution in these patients [see Warnings and Precautions (5.18), Drug Interactions (7), and Clinical Pharmacology (12.3)].

ZYPREXA RELPREVV has not been studied in subjects under 18 years of age [see Warnings and Precautions (5.7)].

Maintenance Treatment — Although no controlled studies have been conducted to determine how long patients should be treated with ZYPREXA RELPREVV, efficacy has been demonstrated over a period of 24 weeks in patients with stabilized schizophrenia. Additionally, oral ZYPREXA has been shown to be effective in maintenance of treatment response in schizophrenia in longer-term use. Patients should be periodically reassessed to determine the need for continued treatment.

Switching from Other Antipsychotics — There are no systematically collected data to specifically address how to switch patients with schizophrenia from other antipsychotics to ZYPREXA RELPREVV.

2.2 Instructions to Reconstitute and Administer ZYPREXA RELPREVV

For deep intramuscular gluteal injection only. Not to be injected intravenously or subcutaneously.

Parenteral drug products should be inspected visually for particulate matter and discoloration prior to administration, whenever solution and container permit.

Step 1: Preparing Materials

Convenience kit includes:

- Single-dose vial of ZYPREXA RELPREVV powder
- 3-mL vial of diluent
- One 3-mL syringe with pre-attached 19-gauge, 1.5-inch (38 mm) Hypodermic Needle-Pro® needle with needle protection device
- Two 19-gauge, 1.5-inch (38 mm) Hypodermic Needle-Pro needles with needle protection device— For obese patients, a 2-inch (50 mm), 19-gauge or larger needle (not included in convenience kit) may be used for administration.

ZYPREXA RELPREVV must be suspended using only the diluent supplied in the convenience kit.

It is recommended that gloves are used when reconstituting, as ZYPREXA RELPREVV may be irritating to the skin. Flush with water if contact is made with skin.

See additional insert entitled "Instructions to Reconstitute and Administer ZYPREXA RELPREVV" (included) for more information regarding the safe and effective use of the Hypodermic Needle-Pro syringe and needle.

Step 2: Determining Reconstitution Volume

Refer to the table below to determine the amount of diluent to be added to powder for reconstitution of each vial strength.

It is important to note that there is more diluent in the vial than is needed to reconstitute.

Dose | Vial Strength | Diluent to Add
150 mg | 210 mg | 1.3 mL
210 mg | 210 mg | 1.3 mL
300 mg | 300 mg | 1.8 mL
405 mg | 405 mg | 2.3 mL

Step 3: Reconstituting ZYPREXA RELPREVV

Please read the Hypodermic Needle-Pro Instructions for Use before proceeding with Step 3. Failure to follow these instructions may result in a needlestick injury.

Loosen the powder by lightly tapping the vial.

Open the prepackaged Hypodermic Needle-Pro syringe and needle with needle protection device.

Withdraw the pre-determined diluent volume (Step 2) into the syringe.

Inject the diluent into the powder vial.

Withdraw air to equalize the pressure in the vial by pulling back slightly on the plunger in the syringe.

Remove the needle from the vial, holding the vial upright to prevent any loss of material.

Engage the needle safety device (refer to complete Hypodermic Needle-Pro Instructions for Use).

Pad a hard surface to cushion impact (see Figure 1). Tap the vial firmly and repeatedly on the surface until no powder is visible.

Figure 1: Tap firmly to mix.

Visually check the vial for clumps. Unsuspended powder appears as yellow, dry clumps clinging to the vial. Additional tapping may be required if large clumps remain (see Figure 2).

Figure 2: Check for unsuspended powder and repeat tapping if needed.

Shake the vial vigorously until the suspension appears smooth and is consistent in color and texture. The suspended product will be yellow and opaque (see Figure 3).

Figure 3: Vigorously shake vial.

If foam forms, let vial stand to allow foam to dissipate.

If the product is not used right away, it should be shaken vigorously to re-suspend. Reconstituted ZYPREXA RELPREVV remains stable at room temperature for up to 24 hours in the vial.

Step 4: Injecting ZYPREXA RELPREVV

Before administering the injection, confirm there will be someone to accompany the patient after the 3-hour observation period. If this cannot be confirmed, do not give the injection.

Refer to the table below to determine the final volume to inject. Suspension concentration is 150 mg/mL ZYPREXA RELPREVV.

Dose | Final Volume to Inject
150 mg | 1 mL
210 mg | 1.4 mL
300 mg | 2 mL
405 mg | 2.7 mL

Attach a new safety needle to the syringe.

Slowly withdraw the desired amount into the syringe.

Some excess product will remain in the vial.

Engage the needle safety device and remove the needle from syringe.

For administration, select the 19-gauge, 1.5-inch (38 mm) Hypodermic Needle-Pro needle with needle protection device. For obese patients, a 2-inch (50 mm), 19-gauge or larger needle (not included in convenience kit) may be used. To help prevent clogging, a 19-gauge or larger needle must be used.

Attach the new safety needle to the syringe prior to injection. Once the suspension has been removed from the vial, it should be injected immediately.

For deep intramuscular gluteal injection only. Do not inject intravenously or subcutaneously.

Select and prepare a site for injection in the gluteal area.

After insertion of the needle into the muscle, aspirate for several seconds to ensure that no blood appears. If any blood is drawn into the syringe, discard the syringe and the dose and begin with a new convenience kit. The injection should be performed with steady, continuous pressure.

Do not massage the injection site.

Engage the needle safety device.

Dispose of the vials, needles, and syringe appropriately after injection. The vial is for single-dose only.

3 DOSAGE FORMS AND STRENGTHS

ZYPREXA RELPREVV is a powder for suspension for intramuscular use only. ZYPREXA RELPREVV is present as a yellow solid in a glass vial equivalent to 210, 300, or 405 mg olanzapine single-dose per vial. The diluent is a clear, colorless to slightly yellow solution in a glass vial [see Description (11) and How Supplied/Storage and Handling (16)]. The reconstituted suspension will be yellow and opaque [see Dosage and Administration (2.2)].

4 CONTRAINDICATIONS

None.

5 WARNINGS AND PRECAUTIONS

5.1 Post-Injection Delirium/Sedation Syndrome

During premarketing clinical studies of ZYPREXA RELPREVV, adverse events that presented with signs and symptoms consistent with olanzapine overdose, in particular, sedation (including coma) and/or delirium, were reported in patients following an injection of ZYPREXA RELPREVV [see Boxed Warning and Dosage and Administration (2.1)]. These events occurred in <0.1% of injections and in approximately 2% of patients who received injections for up to 46 months. These events were correlated with an unintentional rapid increase in serum olanzapine concentrations to supra-therapeutic ranges in some cases. While a rapid and greater than expected increase in serum olanzapine concentration has been observed in some patients with these events, the exact mechanism by which the drug was unintentionally introduced into the blood stream is not known. Clinical signs and symptoms included dizziness, confusion, disorientation, slurred speech, altered gait, difficulty ambulating, weakness, agitation, extrapyramidal symptoms, hypertension, convulsion, and reduced level of consciousness ranging from mild sedation to coma. Time after injection to event ranged from soon after injection to greater than 3 hours after injection. The majority of patients were hospitalized and some required supportive care, including intubation, in several cases. All patients had largely recovered by 72 hours. The risk of an event is the same at each injection, so the risk per patient is cumulative (i.e., increases with the number of injections) [see Overdosage (10.1)].

Healthcare professionals are advised to discuss this potential risk with patients each time they prescribe and administer ZYPREXA RELPREVV [see Patient Counseling Information (17)].

5.2 Prescribing and Distribution Program for ZYPREXA RELPREVV

ZYPREXA RELPREVV is available only through a restricted distribution program [see Boxed Warning, Indications and Usage (1), and Patient Counseling Information (17)]. ZYPREXA RELPREVV must not be dispensed directly to a patient. For a patient to receive treatment, the prescriber, healthcare facility, patient, and pharmacy must all be enrolled in the ZYPREXA RELPREVV Patient Care Program. To enroll, call 1-877-772-9390.

ZYPREXA RELPREVV must be administered in a registered healthcare facility (such as a hospital, clinic, residential treatment center, or community healthcare center) with ready access to emergency response services. After each ZYPREXA RELPREVV injection, a healthcare professional must continuously observe the patient at the healthcare facility for at least 3 hours and must confirm that the patient is alert, oriented, and absent of any signs and symptoms of post-injection delirium/sedation syndrome prior to being released. All patients must be accompanied to their destination upon leaving the facility. For the remainder of the day of each injection, patients should not drive or operate heavy machinery, and should be advised to be vigilant for symptoms of post-injection delirium/sedation syndrome and be able to obtain medical assistance if needed. If post-injection delirium/sedation syndrome is suspected, close medical supervision and monitoring should be instituted in a facility capable of resuscitation [see Overdosage (10)]. If parenteral benzodiazepines are required for patient management during an event of post-injection delirium/sedation syndrome, careful evaluation of clinical status for excessive sedation and cardiorespiratory depression is recommended.

5.3 Elderly Patients with Dementia-Related Psychosis

Increased Mortality

Elderly patients with dementia-related psychosis treated with antipsychotic drugs are at an increased risk of death. ZYPREXA RELPREVV is not approved for the treatment of patients with dementia-related psychosis [see Boxed Warning, Use in Specific Populations (8.5), and Patient Counseling Information (17)].

In placebo-controlled oral olanzapine clinical trials of elderly patients with dementia-related psychosis, the incidence of death in olanzapine-treated patients was significantly greater than placebo-treated patients (3.5% vs 1.5%, respectively).

Cerebrovascular Adverse Events (CVAE), Including Stroke

Cerebrovascular adverse events (e.g., stroke, transient ischemic attack), including fatalities, were reported in patients in trials of oral olanzapine in elderly patients with dementia-related psychosis. In placebo-controlled trials, there was a significantly higher incidence of cerebrovascular adverse events in patients treated with oral olanzapine compared to patients treated with placebo. ZYPREXA RELPREVV is not approved for the treatment of patients with dementia-related psychosis [see Boxed Warning and Patient Counseling Information (17)].

5.4 Suicide

The possibility of a suicide attempt is inherent in schizophrenia, and close supervision of high-risk patients should accompany drug therapy.

5.5 Neuroleptic Malignant Syndrome (NMS)

A potentially fatal symptom complex sometimes referred to as Neuroleptic Malignant Syndrome (NMS) has been reported in association with administration of antipsychotic drugs, including olanzapine. Clinical manifestations of NMS are hyperpyrexia, muscle rigidity, altered mental status and evidence of autonomic instability (irregular pulse or blood pressure, tachycardia, diaphoresis and cardiac dysrhythmia). Additional signs may include elevated creatinine phosphokinase, myoglobinuria (rhabdomyolysis), and acute renal failure.

The diagnostic evaluation of patients with this syndrome is complicated. In arriving at a diagnosis, it is important to exclude cases where the clinical presentation includes both serious medical illness (e.g., pneumonia, systemic infection, etc.) and untreated or inadequately treated extrapyramidal signs and symptoms (EPS). Other important considerations in the differential diagnosis include central anticholinergic toxicity, heat stroke, drug fever, and primary central nervous system pathology.

The management of NMS should include: 1) immediate discontinuation of antipsychotic drugs and other drugs not essential to concurrent therapy; 2) intensive symptomatic treatment and medical monitoring; and 3) treatment of any concomitant serious medical problems for which specific treatments are available. There is no general agreement about specific pharmacological treatment regimens for NMS.

If a patient requires antipsychotic drug treatment after recovery from NMS, the potential reintroduction of drug therapy should be carefully considered and tolerability with oral olanzapine should be established prior to initiating treatment with ZYPREXA RELPREVV [see Dosage and Administration (2.1)]. The patient should be carefully monitored, since recurrences of NMS have been reported [see Patient Counseling Information (17)].

5.6 Drug Reaction with Eosinophilia and Systemic Symptoms (DRESS)

Drug reaction with eosinophilia and systemic symptoms (DRESS) has been reported with olanzapine exposure. DRESS may present with a cutaneous reaction (such as rash or exfoliative dermatitis), eosinophilia, fever, and/or lymphadenopathy with systemic complications such as hepatitis, nephritis, pneumonitis, myocarditis, and/or pericarditis. DRESS is sometimes fatal. Discontinue ZYPREXA RELPREVV if DRESS is suspected [see Patient Counseling Information (17)].

5.7 Metabolic Changes

Atypical antipsychotic drugs have been associated with metabolic changes including hyperglycemia, dyslipidemia, and weight gain. Metabolic changes may be associated with increased cardiovascular/cerebrovascular risk. Olanzapine's specific metabolic profile is presented below.

Hyperglycemia and Diabetes Mellitus

Healthcare providers should consider the risks and benefits when prescribing olanzapine to patients with an established diagnosis of diabetes mellitus, or having borderline increased blood glucose level (fasting 100-126 mg/dL, nonfasting 140-200 mg/dL). Patients taking olanzapine should be monitored regularly for worsening of glucose control. Patients starting treatment with olanzapine should undergo fasting blood glucose testing at the beginning of treatment and periodically during treatment. Any patient treated with atypical antipsychotics should be monitored for symptoms of hyperglycemia including polydipsia, polyuria, polyphagia, and weakness. Patients who develop symptoms of hyperglycemia during treatment with atypical antipsychotics should undergo fasting blood glucose testing. In some cases, hyperglycemia has resolved when the atypical antipsychotic was discontinued; however, some patients required continuation of anti-diabetic treatment despite discontinuation of the suspect drug [see Patient Counseling Information (17)].

Hyperglycemia, in some cases extreme and associated with ketoacidosis or hyperosmolar coma or death, has been reported in patients treated with atypical antipsychotics including olanzapine. Assessment of the relationship between atypical antipsychotic use and glucose abnormalities is complicated by the possibility of an increased background risk of diabetes mellitus in patients with schizophrenia and the increasing incidence of diabetes mellitus in the general population. Epidemiological studies suggest an increased risk of treatment-emergent hyperglycemia-related adverse reactions in patients treated with the atypical antipsychotics. While relative risk estimates are inconsistent, the association between atypical antipsychotics and increases in glucose levels appears to fall on a continuum and olanzapine appears to have a greater association than some other atypical antipsychotics.

Mean increases in blood glucose have been observed in patients treated (median exposure of 9.2 months) with olanzapine in phase 1 of the Clinical Antipsychotic Trials of Intervention Effectiveness (CATIE). The mean increase of serum glucose (fasting and nonfasting samples) from baseline to the average of the 2 highest serum concentrations was 15.0 mg/dL.

In a study of healthy volunteers, subjects who received olanzapine (N=22) for 3 weeks had a mean increase compared to baseline in fasting blood glucose of 2.3 mg/dL. Placebo-treated subjects (N=19) had a mean increase in fasting blood glucose compared to baseline of 0.34 mg/dL.

Olanzapine Monotherapy in Adults — In an analysis of 5 placebo-controlled adult olanzapine monotherapy studies with a median treatment duration of approximately 3 weeks, olanzapine was associated with a greater mean change in fasting glucose levels compared to placebo (2.76 mg/dL versus 0.17 mg/dL). The difference in mean changes between olanzapine and placebo was greater in patients with evidence of glucose dysregulation at baseline (patients diagnosed with diabetes mellitus or related adverse reactions, patients treated with anti-diabetic agents, patients with a baseline random glucose level ≥200 mg/dL, and/or a baseline fasting glucose level ≥126 mg/dL).

Olanzapine-treated patients had a greater mean HbA1c increase from baseline of 0.04% (median exposure 21 days), compared to a mean HbA1c decrease of 0.06% in placebo-treated subjects (median exposure 17 days).

In an analysis of 8 placebo-controlled studies (median treatment exposure 4-5 weeks), 6.1% of olanzapine-treated subjects (N=855) had treatment-emergent glycosuria compared to 2.8% of placebo-treated subjects (N=599). Table 2 shows short-term and long-term changes in fasting glucose levels from adult olanzapine monotherapy studies.

Table 2: Changes in Fasting Glucose Levels from Adult Olanzapine Monotherapy Studies
 |  |  | Up to 12 weeks exposure |  | At least 48 weeks exposure
Laboratory Analyte | Category Change (at least once) from Baseline | Treatment Arm | N | Patients | N | Patients
 | Normal to High | Olanzapine | 543 | 2.2% | 345 | 12.8%
Fasting | (<100 mg/dL to ≥126 mg/dL) | Placebo | 293 | 3.4% | NAa | NAa
Glucose | Borderline to High | Olanzapine | 178 | 17.4% | 127 | 26.0%
 | (≥100 mg/dL and <126 mg/dL to ≥126 mg/dL) | Placebo | 96 | 11.5% | NAa | NAa
a Not Applicable.

The mean change in fasting glucose for patients exposed at least 48 weeks was 4.2 mg/dL (N=487). In analyses of patients who completed 9-12 months of olanzapine therapy, mean change in fasting and nonfasting glucose levels continued to increase over time.

Olanzapine Monotherapy in Adolescents — The safety and efficacy of ZYPREXA RELPREVV have not been established in patients under the age of 18 years.

In an analysis of 3 placebo-controlled oral olanzapine monotherapy studies of adolescent patients (13-17 years), including those with schizophrenia (6 weeks) or bipolar I disorder (manic or mixed episodes) (3 weeks), olanzapine was associated with a greater mean change from baseline in fasting glucose levels compared to placebo (2.68 mg/dL versus -2.59 mg/dL). The mean change in fasting glucose for adolescents exposed at least 24 weeks was 3.1 mg/dL (N=121). Table 3 shows short-term and long-term changes in fasting blood glucose from adolescent oral olanzapine monotherapy studies.

Table 3: Changes in Fasting Glucose Levels from Adolescent Oral Olanzapine Monotherapy Studies
 |  |  | Up to 12 weeks exposure |  | At least 24 weeks exposure
Laboratory Analyte | Category Change (at least once) from Baseline | Treatment Arm | N | Patients | N | Patients
 | Normal to High | Olanzapine | 124 | 0% | 108 | 0.9%
Fasting | (<100 mg/dL to ≥126 mg/dL) | Placebo | 53 | 1.9% | NAa | NAa
Glucose | Borderline to High | Olanzapine | 14 | 14.3% | 13 | 23.1%
 | (≥100 mg/dL and <126 mg/dL to ≥126 mg/dL) | Placebo | 13 | 0% | NAa | NAa
a Not Applicable.

Dyslipidemia

Undesirable alterations in lipids have been observed with olanzapine use. Clinical monitoring, including baseline and periodic follow-up lipid evaluations in patients using olanzapine, is recommended [see Patient Counseling Information (17)].

Clinically significant, and sometimes very high (>500 mg/dL), elevations in triglyceride levels have been observed with olanzapine use. Modest mean increases in total cholesterol have also been seen with olanzapine use.

Olanzapine Monotherapy in Adults — In an analysis of 5 placebo-controlled olanzapine monotherapy studies with treatment duration up to 12 weeks, olanzapine-treated patients had increases from baseline in mean fasting total cholesterol, LDL cholesterol, and triglycerides of 5.3 mg/dL, 3.0 mg/dL, and 20.8 mg/dL respectively compared to decreases from baseline in mean fasting total cholesterol, LDL cholesterol, and triglycerides of 6.1 mg/dL, 4.3 mg/dL, and 10.7 mg/dL for placebo-treated patients. For fasting HDL cholesterol, no clinically meaningful differences were observed between olanzapine-treated patients and placebo-treated patients. Mean increases in fasting lipid values (total cholesterol, LDL cholesterol, and triglycerides) were greater in patients without evidence of lipid dysregulation at baseline, where lipid dysregulation was defined as patients diagnosed with dyslipidemia or related adverse reactions, patients treated with lipid lowering agents, or patients with high baseline lipid levels.

In long-term studies (at least 48 weeks), patients had increases from baseline in mean fasting total cholesterol, LDL cholesterol, and triglycerides of 5.6 mg/dL, 2.5 mg/dL, and 18.7 mg/dL, respectively, and a mean decrease in fasting HDL cholesterol of 0.16 mg/dL. In an analysis of patients who completed 12 months of therapy, the mean nonfasting total cholesterol did not increase further after approximately 4-6 months.

The proportion of patients who had changes (at least once) in total cholesterol, LDL cholesterol or triglycerides from normal or borderline to high, or changes in HDL cholesterol from normal or borderline to low, was greater in long-term studies (at least 48 weeks) as compared with short-term studies. Table 4 shows categorical changes in fasting lipids values.

Table 4: Changes in Fasting Lipids Values from Adult Olanzapine Monotherapy Studies
 |  |  | Up to 12 weeks exposure |  | At least 48 weeks exposure
Laboratory Analyte | Category Change (at least once) from Baseline | Treatment Arm | N | Patients | N | Patients
 | Increase by ≥50 mg/dL | Olanzapine | 745 | 39.6% | 487 | 61.4%
 |  | Placebo | 402 | 26.1% | NAa | NAa
Fasting | Normal to High | Olanzapine | 457 | 9.2% | 293 | 32.4%
Triglycerides | (<150 mg/dL to ≥200 mg/dL) | Placebo | 251 | 4.4% | NAa | NAa
 | Borderline to High | Olanzapine | 135 | 39.3% | 75 | 70.7%
 | (≥150 mg/dL and <200 mg/dL to ≥200 mg/dL) | Placebo | 65 | 20.0% | NAa | NAa
 | Increase by ≥40 mg/dL | Olanzapine | 745 | 21.6% | 489 | 32.9%
 |  | Placebo | 402 | 9.5% | NAa | NAa
Fasting Total | Normal to High | Olanzapine | 392 | 2.8% | 283 | 14.8%
Cholesterol | (<200 mg/dL to ≥240 mg/dL) | Placebo | 207 | 2.4% | NAa | NAa
 | Borderline to High | Olanzapine | 222 | 23.0% | 125 | 55.2%
 | (≥200 mg/dL and <240 mg/dL to ≥240 mg/dL) | Placebo | 112 | 12.5% | NAa | NAa
 | Increase by ≥30 mg/dL | Olanzapine | 536 | 23.7% | 483 | 39.8%
 |  | Placebo | 304 | 14.1% | NAa | NAa
Fasting LDL | Normal to High | Olanzapine | 154 | 0% | 123 | 7.3%
Cholesterol | (<100 mg/dL to ≥160 mg/dL) | Placebo | 82 | 1.2% | NAa | NAa
 | Borderline to High | Olanzapine | 302 | 10.6% | 284 | 31.0%
 | (≥100 mg/dL and <160 mg/dL to ≥160 mg/dL) | Placebo | 173 | 8.1% | NAa | NAa
a Not Applicable.

In phase 1 of the Clinical Antipsychotic Trials of Intervention Effectiveness (CATIE), over a median exposure of 9.2 months, the mean increase in triglycerides in patients taking olanzapine was 40.5 mg/dL. In phase 1 of CATIE, the mean increase in total cholesterol was 9.4 mg/dL.

Dose group differences with respect to increases in fasting triglycerides have been observed. In a 24-week randomized, double-blind, fixed-dose study with ZYPREXA RELPREVV, statistically significant differences among dose groups have been observed for fasting triglycerides. Incidence of changes from normal to high levels of fasting triglycerides at any time during the trial indicated significant differences between the highest dose group (300 mg/2 weeks, 24.5% [13/53]) and the lower dose groups (150 mg/2 weeks, 6.5% [4/62]; 405 mg/4 weeks, 9.8% [13/133]).

Olanzapine Monotherapy in Adolescents — The safety and efficacy of ZYPREXA RELPREVV have not been established in patients under the age of 18 years.

In an analysis of 3 placebo-controlled oral olanzapine monotherapy studies of adolescents (13-17 years), including those with schizophrenia (6 weeks) or bipolar I disorder (manic or mixed episodes) (3 weeks), olanzapine-treated adolescents had increases from baseline in mean fasting total cholesterol, LDL cholesterol, and triglycerides of 12.9 mg/dL, 6.5 mg/dL, and 28.4 mg/dL, respectively, compared to increases from baseline in mean fasting total cholesterol and LDL cholesterol of 1.3 mg/dL and 1.0 mg/dL, and a decrease in triglycerides of 1.1 mg/dL for placebo-treated adolescents. For fasting HDL cholesterol, no clinically meaningful differences were observed between olanzapine-treated adolescents and placebo-treated adolescents.

In long-term studies (at least 24 weeks), adolescents had increases from baseline in mean fasting total cholesterol, LDL cholesterol, and triglycerides of 5.5 mg/dL, 5.4 mg/dL, and 20.5 mg/dL, respectively, and a mean decrease in fasting HDL cholesterol of 4.5 mg/dL. Table 5 shows categorical changes in fasting lipids values in adolescents.

Table 5: Changes in Fasting Lipids Values from Adolescent Oral Olanzapine Monotherapy Studies
 |  |  | Up to 6 weeks exposure |  | At least 24 weeks exposure
Laboratory Analyte | Category Change (at least once) from Baseline | Treatment Arm | N | Patients | N | Patients
 | Increase by ≥50 mg/dL | Olanzapine | 138 | 37.0% | 122 | 45.9%
 |  | Placebo | 66 | 15.2% | NAa | NAa
Fasting | Normal to High | Olanzapine | 67 | 26.9% | 66 | 36.4%
Triglycerides | (<90 mg/dL to >130 mg/dL) | Placebo | 28 | 10.7% | NAa | NAa
 | Borderline to High | Olanzapine | 37 | 59.5% | 31 | 64.5%
 | (≥90 mg/dL and ≤130 mg/dL to >130 mg/dL) | Placebo | 17 | 35.3% | NAa | NAa
 | Increase by ≥40 mg/dL | Olanzapine | 138 | 14.5% | 122 | 14.8%
 |  | Placebo | 66 | 4.5% | NAa | NAa
Fasting Total | Normal to High | Olanzapine | 87 | 6.9% | 78 | 7.7%
Cholesterol | (<170 mg/dL to ≥200 mg/dL) | Placebo | 43 | 2.3% | NAa | NAa
 | Borderline to High | Olanzapine | 36 | 38.9% | 33 | 57.6%
 | (≥170 mg/dL and <200 mg/dL to ≥200 mg/dL) | Placebo | 13 | 7.7% | NAa | NAa
 | Increase by ≥30 mg/dL | Olanzapine | 137 | 17.5% | 121 | 22.3%
 |  | Placebo | 63 | 11.1% | NAa | NAa
Fasting LDL | Normal to High | Olanzapine | 98 | 5.1% | 92 | 10.9%
Cholesterol | (<110 mg/dL to ≥130 mg/dL) | Placebo | 44 | 4.5% | NAa | NAa
 | Borderline to High | Olanzapine | 29 | 48.3% | 21 | 47.6%
 | (≥110 mg/dL and <130 mg/dL to ≥130 mg/dL) | Placebo | 9 | 0% | NAa | NAa
a Not Applicable.

Weight Gain

Potential consequences of weight gain should be considered prior to starting olanzapine. Patients receiving olanzapine should receive regular monitoring of weight [see Patient Counseling Information (17)].

Olanzapine Monotherapy in Adults — In an analysis of 13 placebo-controlled olanzapine monotherapy studies, olanzapine-treated patients gained an average of 2.6 kg (5.7 lb) compared to an average 0.3 kg (0.6 lb) weight loss in placebo-treated patients with a median exposure of 6 weeks; 22.2% of olanzapine-treated patients gained at least 7% of their baseline weight, compared to 3% of placebo-treated patients, with a median exposure to event of 8 weeks; 4.2% of olanzapine-treated patients gained at least 15% of their baseline weight, compared to 0.3% of placebo-treated patients, with a median exposure to event of 12 weeks. Clinically significant weight gain was observed across all baseline Body Mass Index (BMI) categories. Discontinuation due to weight gain occurred in 0.2% of olanzapine-treated patients and in 0% of placebo-treated patients.

In long-term studies (at least 48 weeks), the mean weight gain was 5.6 kg (12.3 lb) (median exposure of 573 days, N=2021). The percentages of patients who gained at least 7%, 15%, or 25% of their baseline body weight with long-term exposure were 64%, 32%, and 12%, respectively. Discontinuation due to weight gain occurred in 0.4% of olanzapine-treated patients following at least 48 weeks of exposure.

Table 6 includes data on adult weight gain with olanzapine pooled from 86 clinical trials. The data in each column represent data for those patients who completed treatment periods of the durations specified.

Table 6: Weight Gain with Olanzapine Use in Adults
 | 6 Weeks | 6 Months | 12 Months | 24 Months | 36 Months
Amount Gained | (N=7465) | (N=4162) | (N=1345) | (N=474) | (N=147)
kg (lb) | (%) | (%) | (%) | (%) | (%)
≤0 | 26.2 | 24.3 | 20.8 | 23.2 | 17.0
0 to ≤5 (0-11 lb) | 57.0 | 36.0 | 26.0 | 23.4 | 25.2
>5 to ≤10 (11-22 lb) | 14.9 | 24.6 | 24.2 | 24.1 | 18.4
>10 to ≤15 (22-33 lb) | 1.8 | 10.9 | 14.9 | 11.4 | 17.0
>15 to ≤20 (33-44 lb) | 0.1 | 3.1 | 8.6 | 9.3 | 11.6
>20 to ≤25 (44-55 lb) | 0 | 0.9 | 3.3 | 5.1 | 4.1
>25 to ≤30 (55-66 lb) | 0 | 0.2 | 1.4 | 2.3 | 4.8
>30 (>66 lb) | 0 | 0.1 | 0.8 | 1.2 | 2

Dose group differences with respect to weight gain have been observed in some studies. In a 24-week randomized, double-blind, fixed-dose study with ZYPREXA RELPREVV, mean baseline-to-endpoint increase in weight (150 mg/2 weeks, n=140: 0.67 kg; 405 mg/4 weeks, n=315: 0.89 kg; 300 mg/2 weeks, n=140: 1.70 kg) was observed with significant differences between the lowest and highest dose groups (150 vs 300 mg/2 weeks). In a single 8-week randomized, double-blind, fixed-dose study comparing 10 (N=199), 20 (N=200) and 40 (N=200) mg/day of oral olanzapine in adult patients with schizophrenia or schizoaffective disorder, mean baseline to endpoint increase in weight (10 mg/day: 1.9 kg; 20 mg/day: 2.3 kg; 40 mg/day: 3 kg) was observed with significant differences between 10 vs 40 mg/day.

Olanzapine Monotherapy in Adolescents — The safety and efficacy of ZYPREXA RELPREVV have not been established in patients under the age of 18 years.

Mean increase in weight in adolescents was greater than in adults. In 4 placebo-controlled trials, discontinuation due to weight gain occurred in 1% of olanzapine-treated patients, compared to 0% of placebo-treated patients.

Table 7: Weight Gain with Oral Olanzapine Use in Adolescents from 4 Placebo-Controlled Trials
 | Olanzapine-treated patients | Placebo-treated patients
Mean change in body weight from baseline (median exposure = 3 weeks) | 4.6 kg (10.1 lb) | 0.3 kg (0.7 lb)
Percentage of patients who gained at least 7% of baseline body weight | 40.6% | 9.8%
Percentage of patients who gained at least 7% of baseline body weight | (median exposure to 7% = 4 weeks) | (median exposure to 7% = 8 weeks)
Percentage of patients who gained at least 15% of baseline body weight | 7.1% | 2.7%
Percentage of patients who gained at least 15% of baseline body weight | (median exposure to 15% = 19 weeks) | (median exposure to 15% = 8 weeks)

In long-term studies (at least 24 weeks), the mean weight gain was 11.2 kg (24.6 lb); (median exposure of 201 days, N=179). The percentages of adolescents who gained at least 7%, 15%, or 25% of their baseline body weight with long-term exposure were 89%, 55%, and 29%, respectively. Among adolescent patients, mean weight gain by baseline BMI category was 11.5 kg (25.3 lb), 12.1 kg (26.6 lb), and 12.7 kg (27.9 lb), respectively, for normal (N=106), overweight (N=26) and obese (N=17). Discontinuation due to weight gain occurred in 2.2% of olanzapine-treated patients following at least 24 weeks of exposure.

Table 8 shows data on adolescent weight gain with olanzapine pooled from 6 clinical trials. The data in each column represent data for those patients who completed treatment periods of the durations specified. Little clinical trial data is available on weight gain in adolescents with olanzapine beyond 6 months of treatment.

Table 8: Weight Gain with Olanzapine Use in Adolescents
 | 6 Weeks | 6 Months
Amount Gained | (N=243) | (N=191)
kg (lb) | (%) | (%)
≤0 | 2.9 | 2.1
0 to ≤5 (0-11 lb) | 47.3 | 24.6
>5 to ≤10 (11-22 lb) | 42.4 | 26.7
>10 to ≤15 (22-33 lb) | 5.8 | 22.0
>15 to ≤20 (33-44 lb) | 0.8 | 12.6
>20 to ≤25 (44-55 lb) | 0.8 | 9.4
>25 to ≤30 (55-66 lb) | 0 | 2.1
>30 to ≤35 (66-77 lb) | 0 | 0
>35 to ≤40 (77-88 lb) | 0 | 0
>40 (>88 lb) | 0 | 0.5

5.8 Tardive Dyskinesia

A syndrome of potentially irreversible, involuntary, dyskinetic movements may develop in patients treated with antipsychotic drugs. Although the prevalence of the syndrome appears to be highest among the elderly, especially elderly women, it is impossible to rely upon prevalence estimates to predict, at the inception of antipsychotic treatment, which patients are likely to develop the syndrome. Whether antipsychotic drug products differ in their potential to cause tardive dyskinesia is unknown.

The risk of developing tardive dyskinesia and the likelihood that it will become irreversible are believed to increase as the duration of treatment and the total cumulative dose of antipsychotic drugs administered to the patient increase. However, the syndrome can develop, although much less commonly, after relatively brief treatment periods at low doses or may even arise after discontinuation of treatment.

Tardive dyskinesia may remit, partially or completely, if antipsychotic treatment is withdrawn. Antipsychotic treatment, itself, however, may suppress (or partially suppress) the signs and symptoms of the syndrome and thereby may possibly mask the underlying process. The effect that symptomatic suppression has upon the long-term course of the syndrome is unknown.

Given these considerations, olanzapine should be prescribed in a manner that is most likely to minimize the occurrence of tardive dyskinesia. Chronic antipsychotic treatment should generally be reserved for patients (1) who suffer from a chronic illness that is known to respond to antipsychotic drugs, and (2) for whom alternative, equally effective, but potentially less harmful treatments are not available or appropriate. In patients who do require chronic treatment, the smallest dose and the shortest duration of treatment producing a satisfactory clinical response should be sought. The need for continued treatment should be reassessed periodically.

If signs and symptoms of tardive dyskinesia appear in a patient on olanzapine, drug discontinuation should be considered. However, some patients may require treatment with olanzapine despite the presence of the syndrome.

5.9 Orthostatic Hypotension

ZYPREXA RELPREVV may induce orthostatic hypotension associated with dizziness, tachycardia, bradycardia and, in some patients, syncope, probably reflecting its α1-adrenergic antagonistic properties [see Patient Counseling Information (17)]. Syncope-related adverse reactions were reported in 0.1% of patients treated with ZYPREXA RELPREVV in clinical studies.

From an analysis of the vital sign data in an integrated database of 41 completed clinical studies in adult patients treated with oral olanzapine, orthostatic hypotension was recorded in ≥20% (1277/6030) of patients.

Olanzapine should be used with particular caution in patients with known cardiovascular disease (history of myocardial infarction or ischemia, heart failure, or conduction abnormalities), cerebrovascular disease, and conditions which would predispose patients to hypotension (dehydration, hypovolemia, and treatment with antihypertensive medications) where the occurrence of syncope, or hypotension and/or bradycardia might put the patient at increased medical risk. For patients in this population who have never taken oral olanzapine, tolerability should be established with oral olanzapine prior to initiating treatment with ZYPREXA RELPREVV [see Dosage and Administration (2.1)].

Caution is necessary in patients who receive treatment with other drugs having effects that can induce hypotension, bradycardia, respiratory or central nervous system depression [see Drug Interactions (7)].

5.10 Falls

ZYPREXA RELPREVV may cause somnolence, postural hypotension, motor and sensory instability, which may lead to falls and, consequently, fractures or other injuries. For patients with diseases, conditions, or medications that could exacerbate these effects, complete fall risk assessments when initiating antipsychotic treatment and recurrently for patients on long-term antipsychotic therapy.

5.11 Leukopenia, Neutropenia, and Agranulocytosis

Class Effect — In clinical trial and/or postmarketing experience, events of leukopenia/neutropenia have been reported temporally related to antipsychotic agents, including ZYPREXA. Agranulocytosis has also been reported.

Possible risk factors for leukopenia/neutropenia include pre-existing low white blood cell count (WBC) and history of drug-induced leukopenia/neutropenia. Patients with a history of a clinically significant low WBC or drug induced leukopenia/neutropenia should have their complete blood count (CBC) monitored frequently during the first few months of therapy and discontinuation of ZYPREXA RELPREVV should be considered at the first sign of a clinically significant decline in WBC in the absence of other causative factors.

Patients with clinically significant neutropenia should be carefully monitored for fever or other symptoms or signs of infection and treated promptly if such symptoms or signs occur. Patients with severe neutropenia (absolute neutrophil count <1000/mm^3) should discontinue ZYPREXA RELPREVV and have their WBC followed until recovery.

5.12 Dysphagia

Esophageal dysmotility and aspiration have been associated with antipsychotic drug use. Aspiration pneumonia is a common cause of morbidity and mortality in patients with advanced Alzheimer's disease. Olanzapine is not approved for the treatment of patients with Alzheimer's disease.

5.13 Seizures

During premarketing testing of ZYPREXA RELPREVV, seizures occurred in 0.15% of patients. During premarketing testing of oral olanzapine, seizures occurred in 0.9% of olanzapine-treated patients. There were confounding factors that may have contributed to the occurrence of seizures in many of these cases.

Olanzapine should be used cautiously in patients with a history of seizures or with conditions that potentially lower the seizure threshold, e.g., Alzheimer's dementia. Olanzapine is not approved for the treatment of patients with Alzheimer's disease. Conditions that lower the seizure threshold may be more prevalent in a population of 65 years or older.

5.14 Potential for Cognitive and Motor Impairment

Sedation was a commonly reported adverse reaction associated with ZYPREXA RELPREVV treatment, occurring at an incidence of 8% in ZYPREXA RELPREVV patients compared to 2% in placebo patients. Somnolence and sedation adverse reactions led to discontinuation in 0.6% of patients in the premarketing ZYPREXA RELPREVV database.

Since olanzapine has the potential to impair judgment, thinking, or motor skills, patients should be cautioned about operating hazardous machinery, including automobiles, until they are reasonably certain that olanzapine therapy does not affect them adversely. However, due to the risk of post-injection delirium/sedation syndrome after each injection, patients should not drive or operate heavy machinery for the remainder of the day of each injection [see Dosage and Administration (2.1), Warnings and Precautions (5.1), and Patient Counseling Information (17)].

5.15 Body Temperature Regulation

Disruption of the body's ability to reduce core body temperature has been attributed to antipsychotic agents. Appropriate care is advised when prescribing ZYPREXA RELPREVV for patients who will be experiencing conditions which may contribute to an elevation in core body temperature, e.g., exercising strenuously, exposure to extreme heat, receiving concomitant medication with anticholinergic activity, or being subject to dehydration [see Patient Counseling Information (17)].

5.16 Anticholinergic (antimuscarinic) Effects

Olanzapine exhibits in vitro muscarinic receptor affinity [see Clinical Pharmacology 12.2]. In premarketing clinical trials with oral olanzapine, olanzapine was associated with constipation, dry mouth, and tachycardia, all adverse reactions possibly related to cholinergic antagonism. Such adverse reactions were not often the basis for discontinuations from olanzapine, but olanzapine should be used with caution in patients with a current diagnosis or prior history of urinary retention, clinically significant prostatic hypertrophy, constipation, or a history of paralytic ileus or related conditions. In post marketing experience, the risk for severe adverse reactions (including fatalities) was increased with concomitant use of anticholinergic medications [see Drug Interactions (7.1)].

5.17 Hyperprolactinemia

As with other drugs that antagonize dopamine D2 receptors, olanzapine elevates prolactin levels, and the elevation persists during chronic administration. Hyperprolactinemia may suppress hypothalamic GnRH, resulting in reduced pituitary gonadotropin secretion. This, in turn, may inhibit reproductive function by impairing gonadal steroidogenesis in both female and male patients. Galactorrhea, amenorrhea, gynecomastia, and impotence have been reported in patients receiving prolactin-elevating compounds. Long-standing hyperprolactinemia when associated with hypogonadism may lead to decreased bone density in both female and male subjects.

Tissue culture experiments indicate that approximately one-third of human breast cancers are prolactin dependent in vitro, a factor of potential importance if the prescription of these drugs is contemplated in a patient with previously detected breast cancer. As is common with compounds which increase prolactin release, an increase in mammary gland neoplasia was observed in the oral olanzapine carcinogenicity studies conducted in mice and rats [see Nonclinical Toxicology (13.1)]. Published epidemiologic studies have shown inconsistent results when exploring the potential association between hyperprolactinemia and breast cancer.

In placebo-controlled olanzapine clinical studies (up to 12 weeks), changes from normal to high in prolactin concentrations were observed in 30% of adults treated with olanzapine as compared to 10.5% of adults treated with placebo. In a pooled analysis from clinical studies including 8136 adults treated with olanzapine, potentially associated clinical manifestations included menstrual-related events^1 (2% [49/3240] of females), sexual function-related events^2 (2% [150/8136] of females and males), and breast-related events^3 (0.7% [23/3240] of females, 0.2% [9/4896] of males).

In placebo-controlled olanzapine monotherapy studies in adolescent patients (up to 6 weeks) with schizophrenia or bipolar I disorder (manic or mixed episodes), changes from normal to high in prolactin concentrations were observed in 47% of olanzapine-treated patients compared to 7% of placebo-treated patients. In a pooled analysis from clinical trials including 454 adolescents treated with olanzapine, potentially associated clinical manifestations included menstrual-related events^1 (1% [2/168] of females), sexual function-related events^2 (0.7% [3/454] of females and males), and breast-related events^3 (2% [3/168] of females, 2% [7/286] of males) [see Use in Specific Populations (8.4)].

^1 Based on a search of the following terms: amenorrhea, hypomenorrhea, menstruation delayed, and oligomenorrhea.

^2 Based on a search of the following terms: anorgasmia, delayed ejaculation, erectile dysfunction, decreased libido, loss of libido, abnormal orgasm, and sexual dysfunction.

^3 Based on a search of the following terms: breast discharge, enlargement or swelling, galactorrhea, gynecomastia, and lactation disorder.

Dose group differences with respect to prolactin elevation have been observed in some studies. In a 24-week randomized, double-blind, fixed-dose study with ZYPREXA RELPREVV, statistically significant differences among dose groups were observed for prolactin levels, with a mean baseline-to-endpoint increase observed in the highest dose group (300 mg/2 weeks, n=115: 3.57 ng/mL) relative to mean decreases in the lower dose groups (150 mg/2 weeks, n=109: -5.61 ng/mL; 405 mg/4 weeks, n=259: -2.76 ng/mL). In a single 8-week randomized, double-blind, fixed-dose study comparing 10 (N=199), 20 (N=200) and 40 (N=200) mg/day of oral olanzapine in adult patients with schizophrenia or schizoaffective disorder, incidence of prolactin elevation >24.2 ng/mL (female) or >18.77 ng/mL (male) at any time during the trial (10 mg/day: 31.2%; 20 mg/day: 42.7%; 40 mg/day: 61.1%) indicated significant differences between 10 vs 40 mg/day and 20 vs 40 mg/day.

5.18 Laboratory Tests

Fasting blood glucose testing and lipid profile at the beginning of, and periodically during, treatment is recommended [see Warnings and Precautions (5.7) and Patient Counseling Information (17)].

6 ADVERSE REACTIONS

6.1 Clinical Trials Experience

Because clinical trials are conducted under widely varying conditions, adverse reaction rates observed in the clinical trials of a drug cannot be directly compared to rates in the clinical trials of another drug and may not reflect or predict the rates observed in practice.

The information below for ZYPREXA RELPREVV is derived primarily from a clinical trial database consisting of 2058 patients with approximately 1948 patient years of exposure to ZYPREXA RELPREVV. This database includes safety data from 6 open-label studies and 2 double-blind comparator studies, conducted in patients with schizophrenia or schizoaffective disorder. Additionally, data obtained from patients treated with oral olanzapine are also presented below. Adverse reactions were assessed by the collection of adverse reactions, vital signs, weights, laboratory analytes, ECGs, and the results of physical and ophthalmologic examinations. In the tables and tabulations that follow for ZYPREXA RELPREVV, the MedDRA terminology has been used to classify reported adverse reactions. Data obtained from oral olanzapine studies was reported using the COSTART and MedDRA dictionaries.

The stated frequencies of adverse reactions represent the proportion of individuals who experienced, at least once, a treatment-emergent adverse reaction of the type listed. A reaction was considered treatment emergent if it occurred for the first time or worsened while receiving therapy following baseline evaluation. Reactions listed elsewhere in labeling may not be repeated below. The entire label should be read to gain a complete understanding of the safety profile of ZYPREXA RELPREVV.

The prescriber should be aware that the figures in the tables and tabulations cannot be used to predict the incidence of side effects in the course of usual medical practice where patient characteristics and other factors differ from those that prevailed in the clinical trials. Similarly, the cited frequencies cannot be compared with figures obtained from other clinical investigations involving different treatments, uses, and investigators. The cited figures, however, do provide the prescribing healthcare provider with some basis for estimating the relative contribution of drug and nondrug factors to the adverse reaction incidence in the population studied.

Adverse Reactions Associated with Discontinuation of Treatment in a Short-Term, Placebo-Controlled Trial

Overall, there was no difference in the incidence of discontinuation due to adverse reactions between ZYPREXA RELPREVV (4%; 13/306 patients) and placebo (5%; 5/98 patients) in an 8-week trial.

Commonly Observed Adverse Reactions in a Short-Term, Placebo-Controlled Trial

In an 8-week trial, treatment-emergent adverse reactions with an incidence of 5% or greater in at least one of the ZYPREXA RELPREVV treatment groups (210 mg/2 weeks, 405 mg/4 weeks, or 300 mg/2 weeks) and greater than placebo were: headache, sedation, weight gain, cough, diarrhea, back pain, nausea, somnolence, dry mouth, nasopharyngitis, increased appetite, and vomiting.

Adverse Reactions Occurring at an Incidence of 2% or More among ZYPREXA RELPREVV-Treated Patients in a Short-Term, Placebo-Controlled Trial

Table 9 enumerates the incidence, rounded to the nearest percent, of treatment-emergent adverse reactions that occurred in 2% or more of patients treated with ZYPREXA RELPREVV and with incidence greater than placebo who participated in the 8-week, placebo-controlled trial.

Table 9: Treatment-Emergent Adverse Reactions: Incidence in a Short-Term, Placebo-Controlled Clinical Trial with ZYPREXA RELPREVV
 | Percentage of Patients Reporting Adverse Event
 |  | ZYPREXA RELPREVV | ZYPREXA RELPREVV | ZYPREXA RELPREVV
 | Placebo | 405 mg/4 wks | 210 mg/2 wks | 300 mg/2 wks
Body System/Adverse Reaction | (N=98) | (N=100) | (N=106) | (N=100)
Ear and Labyrinth Disorders
Ear pain | 2 | 1 | 1 | 4
Gastrointestinal Disorders
Abdominal paina | 2 | 3 | 3 | 3
Diarrhea | 4 | 2 | 7 | 5
Dry mouth | 1 | 2 | 6 | 4
Flatulence | 0 | 2 | 2 | 1
Nausea | 2 | 5 | 5 | 4
Toothache | 0 | 3 | 4 | 3
Vomiting | 2 | 6 | 1 | 2
General Disorders and Administration Site Conditions
Fatigue | 2 | 4 | 2 | 3
Injection site pain | 0 | 2 | 3 | 2
Pain | 0 | 0 | 2 | 3
Pyrexia | 0 | 2 | 0 | 0
Infections and Infestations
Nasopharyngitis | 2 | 3 | 6 | 1
Tooth infectionb | 0 | 4 | 0 | 0
Upper respiratory tract infection | 2 | 3 | 1 | 4
Viral infection | 0 | 0 | 0 | 2
Injury, Poisoning and Procedural Complications
Procedural pain | 0 | 2 | 0 | 0
Investigations
Electrocardiogram QT-corrected interval prolonged | 1 | 0 | 0 | 2
Hepatic enzyme increasedc | 1 | 4 | 1 | 3
Weight increased | 5 | 5 | 6 | 7
Metabolism and Nutrition Disorders
Increased appetite | 0 | 1 | 4 | 6
Musculoskeletal and Connective Tissue Disorders
Arthralgia | 0 | 3 | 3 | 3
Back pain | 4 | 4 | 3 | 5
Muscle spasms | 0 | 3 | 1 | 2
Musculoskeletal stiffness | 1 | 1 | 4 | 4
Nervous System Disorders
Dizziness | 2 | 4 | 4 | 1
Dysarthria | 0 | 0 | 1 | 2
Headached | 8 | 13 | 15 | 18
Sedatione | 7 | 13 | 8 | 13
Tremor | 1 | 3 | 0 | 1
Psychiatric Disorders
Abnormal dreams | 0 | 0 | 0 | 2
Hallucination, auditory | 2 | 3 | 1 | 0
Restlessness | 2 | 2 | 3 | 1
Sleep disorder | 1 | 0 | 0 | 2
Thinking abnormal | 1 | 3 | 0 | 0
Reproductive System and Breast Disorders
Vaginal discharge | 0 | 0 | 4 | 4
Respiratory, Thoracic and Mediastinal Disorders
Cough | 5 | 3 | 5 | 9
Nasal congestionf | 3 | 2 | 1 | 7
Pharyngolaryngeal pain | 2 | 2 | 3 | 3
Sneezing | 0 | 0 | 0 | 2
Skin and Subcutaneous Tissue Disorders
Acne | 0 | 2 | 0 | 2
Vascular Disorders
Hypertension | 0 | 3 | 2 | 0
a The term abdominal pain upper was combined under abdominal pain.
b The term tooth abscess was combined under tooth infection.
c The terms alanine aminotransferase increased, aspartate aminotransferase increased, and gamma-glutamyltransferase increased were combined under hepatic enzyme increased.
d The term tension headache was combined under headache.
e The term somnolence was combined under sedation.
f The term sinus congestion was combined under nasal congestion.

Dose Dependency of Adverse Reactions

Dose group differences have been observed for weight, fasting triglycerides and prolactin elevation for ZYPREXA RELPREVV [see Warnings and Precautions (5.7, 5.17)].

A dose group difference for oral olanzapine has been observed for fatigue, dizziness, weight gain and prolactin elevation. In a single 8-week randomized, double-blind, fixed-dose study comparing 10 (N=199), 20 (N=200) and 40 (N=200) mg/day of oral olanzapine in adult patients with schizophrenia or schizoaffective disorder, incidence of fatigue (10 mg/day: 1.5%; 20 mg/day: 2.1%; 40 mg/day: 6.6%) was observed with significant differences between 10 vs 40 and 20 vs 40 mg/day. The incidence of dizziness (10 mg/day: 2.6%; 20 mg/day: 1.6%; 40 mg/day: 6.6%) was observed with significant differences between 20 vs 40 mg. Dose group differences were also noted for weight gain and prolactin elevation [see Warnings and Precautions (5.7, 5.17)].

Extrapyramidal Symptoms

The following table enumerates the percentage of patients with treatment-emergent extrapyramidal symptoms as assessed by categorical analyses of formal rating scales during acute therapy in a controlled clinical trial comparing oral olanzapine at 3 fixed doses with placebo in the treatment of schizophrenia in a 6-week trial.

Table 10: Treatment-Emergent Extrapyramidal Symptoms Assessed by Rating Scales Incidence in a Fixed Dosage Range, Placebo-Controlled Clinical Trial of Oral Olanzapine in Schizophrenia — Acute Phase
 | Percentage of Patients Reporting Event
 |  | Olanzapine | Olanzapine | Olanzapine
 | Placebo | 5 ± 2.5 mg/day | 10 ± 2.5 mg/day | 15 ± 2.5 mg/day
Parkinsonisma | 15 | 14 | 12 | 14
Akathisiab | 23 | 16 | 19 | 27
a Percentage of patients with a Simpson-Angus Scale total score >3.
b Percentage of patients with a Barnes Akathisia Scale global score ≥2.

The following table enumerates the percentage of patients with treatment-emergent extrapyramidal symptoms as assessed by spontaneously reported adverse reactions during acute therapy in the same controlled clinical trial comparing olanzapine at 3 fixed doses with placebo in the treatment of schizophrenia in a 6-week trial.

Table 11: Treatment-Emergent Extrapyramidal Symptoms Assessed by Adverse Reactions Incidence in a Fixed Dosage Range, Placebo-Controlled Clinical Trial of Oral Olanzapine in Schizophrenia — Acute Phase
 | Percentage of Patients Reporting Event
 |  | Olanzapine | Olanzapine | Olanzapine
 | Placebo | 5 ± 2.5 mg/day | 10 ± 2.5 mg/day | 15 ± 2.5 mg/day
 | (N=68) | (N=65) | (N=64) | (N=69)
Dystonic eventsa | 1 | 3 | 2 | 3
Parkinsonism eventsb | 10 | 8 | 14 | 20
Akathisia eventsc | 1 | 5 | 11 | 10
Dyskinetic eventsd | 4 | 0 | 2 | 1
Residual eventse | 1 | 2 | 5 | 1
Any extrapyramidal event | 16 | 15 | 25 | 32
a Patients with the following COSTART terms were counted in this category: dystonia, generalized spasm, neck rigidity, oculogyric crisis, opisthotonos, torticollis.
b Patients with the following COSTART terms were counted in this category: akinesia, cogwheel rigidity, extrapyramidal syndrome, hypertonia, hypokinesia, masked facies, tremor.
c Patients with the following COSTART terms were counted in this category: akathisia, hyperkinesia.
d Patients with the following COSTART terms were counted in this category: buccoglossal syndrome, choreoathetosis, dyskinesia, tardive dyskinesia.
e Patients with the following COSTART terms were counted in this category: movement disorder, myoclonus, twitching.

Dystonia, Class Effect: Symptoms of dystonia, prolonged abnormal contractions of muscle groups, may occur in susceptible individuals during the first few days of treatment. Dystonic symptoms include: spasm of the neck muscles, sometimes progressing to tightness of the throat, swallowing difficulty, difficulty breathing, and/or protrusion of the tongue. While these symptoms can occur at low doses, the frequency and severity are greater with high potency and at higher doses of first generation antipsychotic drugs. In general, an elevated risk of acute dystonia may be observed in males and younger age groups receiving antipsychotics; however, events of dystonia have been reported infrequently (<1%) with olanzapine use.

Other Adverse Reactions

Local Injection Site Reactions

Eleven ZYPREXA RELPREVV-treated patients (3.6%) and 0 placebo-treated patients experienced treatment-emergent injection-related adverse reactions (injection site pain, buttock pain, injection site mass, induration, injection site induration) in the placebo-controlled database. The most frequently occurring treatment-emergent adverse reaction was injection site pain (2.3% ZYPREXA RELPREVV-treated; 0% placebo-treated).

Other Adverse Reactions Observed During the Clinical Trial Evaluation of Olanzapine for Extended-Release Injectable Suspension

Injection site abscess has been reported in clinical trials with ZYPREXA RELPREVV therapy. Isolated cases required surgical intervention.

Commonly Observed Adverse Reactions During the Clinical Trial Evaluation of Oral Olanzapine

In clinical trials of oral olanzapine monotherapy for the treatment of schizophrenia in adult patients, treatment-emergent adverse reactions with an incidence of 5% or greater in the olanzapine treatment arm and at least twice that of placebo were: postural hypotension, constipation, weight gain, dizziness, personality disorder, and akathisia.

Other Adverse Reactions Observed During the Clinical Trial Evaluation of Oral Olanzapine

Following is a list of treatment-emergent adverse reactions reported by patients treated with oral olanzapine (at multiple doses ≥1 mg/day) in clinical trials. This listing is not intended to include reactions (1) already listed in previous tables or elsewhere in labeling, (2) for which a drug cause was remote, (3) which were so general as to be uninformative, (4) which were not considered to have significant clinical implications, or (5) which occurred at a rate equal to or less than placebo. Reactions are classified by body system using the following definitions: frequent adverse reactions are those occurring in at least 1/100 patients; infrequent adverse reactions are those occurring in 1/100 to 1/1000 patients; rare adverse reactions are those occurring in fewer than 1/1000 patients.

Body as a Whole — Infrequent: chills, face edema, photosensitivity reaction, suicide attempt^1; Rare: chills and fever, hangover effect, sudden death^1.

Cardiovascular System — Infrequent: cerebrovascular accident, vasodilatation.

Digestive System — Infrequent: abdominal distension, nausea and vomiting, tongue edema; Rare: ileus, intestinal obstruction, liver fatty deposit.

Hemic and Lymphatic System — Infrequent: thrombocytopenia.

Metabolic and Nutritional Disorders — Frequent: alkaline phosphatase increased; Infrequent: bilirubinemia, hypoproteinemia.

Musculoskeletal System — Rare: osteoporosis.

Nervous System — Infrequent: ataxia, dysarthria, libido decreased, stupor; Rare: coma.

Respiratory System — Infrequent: epistaxis; Rare: lung edema.

Skin and Appendages — Infrequent: alopecia.

Special Senses — Infrequent: abnormality of accommodation, dry eyes; Rare: mydriasis.

Urogenital System — Infrequent: amenorrhea^2, breast pain, decreased menstruation, impotence^2, increased menstruation^2, menorrhagia^2, metrorrhagia^2, polyuria^2, urinary frequency, urinary retention, urinary urgency, urination impaired.

^1 These terms represent serious adverse events but do not meet the definition for adverse drug reactions. They are included here because of their seriousness.

^2 Adjusted for gender.

Vital Signs and Laboratory Studies

Laboratory Changes

ZYPREXA RELPREVV in Adults: Statistically significant within group mean changes for ZYPREXA RELPREVV, which were also significantly different from placebo, were observed for the following: eosinophils, monocytes, cholesterol, low-density lipoprotein (LDL), triglycerides, and direct bilirubin. There were no statistically significant differences between ZYPREXA RELPREVV and placebo in the incidence of potentially clinically significant changes in any of the laboratory values studied.

Statistically significant within group mean changes for ZYPREXA RELPREVV, which were also significantly different from oral olanzapine (in a 24-week double-blind study), were observed for the following: gamma-glutamyltransferase (GGT) and sodium.

From an analysis of the laboratory data in an integrated database of 41 completed clinical studies in adult patients treated with oral olanzapine, high GGT levels were recorded in ≥1% (88/5245) of patients.

Statistically significant differences were observed between ZYPREXA RELPREVV and oral olanzapine for the incidence of treatment-emergent low platelet count (0% ZYPREXA RELPREVV vs 1% oral olanzapine); and low total bilirubin (2.8% ZYPREXA RELPREVV vs 0.7% for oral olanzapine). There was a statistically significant difference between ZYPREXA RELPREVV and oral olanzapine in potentially clinically significant changes for high leukocyte count (0% ZYPREXA RELPREVV vs 1% oral olanzapine).

Changes in aminotransferases observed with ZYPREXA RELPREVV treatment were similar to those reported with ZYPREXA treatment. In placebo-controlled ZYPREXA RELPREVV studies, clinically significant ALT elevations (≥3 times the upper limit of the normal range) were observed in 2.7% (8/291) of patients exposed to olanzapine compared to 3.2% (3/94) of the placebo patients. None of these patients experienced jaundice. In 3 of these patients, liver enzymes reverted to the normal range despite continued treatment, and in 5 cases enzymes values decreased, but were still above the normal range at the end of therapy.

Within the larger premarketing ZYPREXA RELPREVV database of 1886 patients with baseline ALT ≤90 IU/L, the incidence of ALT elevation to >200 IU/L was 0.8%. None of these patients experienced jaundice or other symptoms attributable to liver impairment and most had transient changes that tended to normalize while ZYPREXA RELPREVV treatment was continued.

From an analysis of the laboratory data in an integrated database of 41 completed clinical studies in adult patients treated with oral olanzapine, elevated uric acid was recorded in ≥3% (171/4641) of patients.

Olanzapine Monotherapy in Adults: An assessment of the premarketing experience for oral olanzapine revealed an association with asymptomatic increases in ALT, AST, and GGT. Within the original premarketing database of about 2400 adult patients with baseline ALT ≤90 IU/L, the incidence of ALT elevations to >200 IU/L was 2% (50/2381). None of these patients experienced jaundice or other symptoms attributable to liver impairment and most had transient changes that tended to normalize while olanzapine treatment was continued.

In placebo-controlled oral olanzapine monotherapy studies in adults, clinically significant ALT elevations (change from <3 times the upper limit of normal [ULN] at baseline to ≥3 times ULN) were observed in 5% (77/1426) of patients exposed to olanzapine compared to 1% (10/1187) of patients exposed to placebo. ALT elevations ≥5 times ULN were observed in 2% (29/1438) of olanzapine-treated patients, compared to 0.3% (4/1196) of placebo-treated patients. ALT values returned to normal, or were decreasing, at last follow-up in the majority of patients who either continued treatment with olanzapine or discontinued olanzapine. No patient with elevated ALT values experienced jaundice, liver failure, or met the criteria for Hy's Rule.

Caution should be exercised in patients with signs and symptoms of hepatic impairment, in patients with pre-existing conditions associated with limited hepatic functional reserve, and in patients who are being treated with potentially hepatotoxic drugs.

Oral olanzapine administration was also associated with increases in serum prolactin [see Warnings and Precautions (5.17)], with an asymptomatic elevation of the eosinophil count in 0.3% of patients, and with an increase in CPK.

ECG Changes — Comparison of ZYPREXA RELPREVV and oral olanzapine, in a 24 week study, revealed no significant differences on ECG changes. Between-group comparisons for pooled placebo-controlled trials revealed no significant oral olanzapine/placebo differences in the proportions of patients experiencing potentially important changes in ECG parameters, including QT, QTc, and PR intervals. Oral olanzapine use was associated with a mean increase in heart rate of 2.4 beats per minute compared to no change among placebo patients. This slight tendency to tachycardia may be related to olanzapine's potential for inducing orthostatic changes [see Warnings and Precautions (5.11)].

6.2 Postmarketing Experience

The following adverse reactions have been identified during post-approval use of ZYPREXA and ZYPREXA RELPREVV. Because these reactions are reported voluntarily from a population of uncertain size, it is difficult to reliably estimate their frequency or evaluate a causal relationship to drug exposure.

Adverse reactions reported since market introduction that were temporally (but not necessarily causally) related to ZYPREXA therapy include the following: allergic reaction (e.g., anaphylactoid reaction, angioedema, pruritus or urticaria), cholestatic or mixed liver injury, diabetic coma, diabetic ketoacidosis, discontinuation reaction (diaphoresis, nausea, or vomiting), drug reaction with eosinophilia and systemic symptoms (DRESS), hepatitis, jaundice, neutropenia, pancreatitis, priapism, rash, restless legs syndrome, rhabdomyolysis, salivary hypersecretion, stuttering^1, venous thromboembolic events (including pulmonary embolism and deep venous thrombosis), fecal incontinence, somnambulism, and syndrome of inappropriate antidiuretic hormone secretion (SIADH). Random cholesterol levels of ≥240 mg/dL and random triglyceride levels of ≥1000 mg/dL have been reported. Additionally, injection site abscess has been reported in postmarketing reports with ZYPREXA RELPREVV therapy. Isolated cases required surgical intervention.

^1 Stuttering was only studied in oral and long acting injection (LAI) formulations.

7 DRUG INTERACTIONS

7.1 Potential for Other Drugs to Affect Olanzapine

Diazepam — The co-administration of diazepam with olanzapine potentiated the orthostatic hypotension observed with olanzapine [see Drug Interactions (7.2)].

Inducers of CYP1A2 — Carbamazepine therapy (200 mg bid) causes an approximately 50% increase in the clearance of olanzapine. This increase is likely due to the fact that carbamazepine is a potent inducer of CYP1A2 activity. Higher daily doses of carbamazepine may cause an even greater increase in olanzapine clearance.

Alcohol — Ethanol (45 mg/70 kg single dose) did not have an effect on olanzapine pharmacokinetics. The co-administration of alcohol (i.e., ethanol) with olanzapine potentiated the orthostatic hypotension observed with olanzapine [see Drug Interactions (7.2)].

Inhibitors of CYP1A2 — Fluvoxamine, a CYP1A2 inhibitor, decreases the clearance of olanzapine. This results in a mean increase in olanzapine Cmax following fluvoxamine of 54% in female nonsmokers and 77% in male smokers. The mean increase in olanzapine AUC is 52% and 108%, respectively. Lower doses of olanzapine should be considered in patients receiving concomitant treatment with fluvoxamine.

Inhibitors of CYP2D6 — Fluoxetine caused a small decrease in olanzapine clearance leading to a minimal change in olanzapine steady-state concentrations and, therefore dose modification is not routinely recommended.

Warfarin — Warfarin (20 mg single dose) did not affect olanzapine pharmacokinetics [see Drug Interactions (7.2)].

Inducers of CYP1A2 or Glucuronyl Transferase Enzymes — Omeprazole and rifampin may cause an increase in olanzapine clearance.

Anticholinergic Drugs — Concomitant treatment with olanzapine and other drugs with anticholinergic activity can increase the risk for severe gastrointestinal adverse reactions related to hypomotility. ZYPREXA RELPREVV should be used with caution in patients receiving medications having anticholinergic (antimuscarinic) effects [see Warnings and Precautions (5.16)].

7.2 Potential for Olanzapine to Affect Other Drugs

CNS Acting Drugs — Given the primary CNS effects of olanzapine, caution should be used when olanzapine is taken in combination with other centrally acting drugs and alcohol.

Antihypertensive Agents — Olanzapine, because of its potential for inducing hypotension, may enhance the effects of certain antihypertensive agents.

Levodopa and Dopamine Agonists — Olanzapine may antagonize the effects of levodopa and dopamine agonists.

Lorazepam (IM) — Co-administration of lorazepam does not significantly affect the pharmacokinetics of olanzapine, unconjugated lorazepam, or total lorazepam. However, this co-administration of lorazepam with olanzapine potentiated the somnolence observed with either drug alone.

Lithium — Multiple doses of olanzapine (10 mg for 8 days) did not influence the kinetics of lithium. Therefore, concomitant olanzapine administration does not require dosage adjustment of lithium.

Valproate — Olanzapine (10 mg daily for 2 weeks) did not affect the steady-state plasma concentrations of valproate. Therefore, concomitant olanzapine administration does not require dosage adjustment of valproate.

Effect of Olanzapine on Drug Metabolizing Enzymes — In vitro studies utilizing human liver microsomes suggest that olanzapine has little potential to inhibit CYP1A2, CYP2C9, CYP2C19, CYP2D6, and CYP3A. Thus, olanzapine is unlikely to cause clinically important drug interactions mediated by these enzymes.

Imipramine — Single doses of olanzapine did not affect the pharmacokinetics of imipramine or its active metabolite desipramine.

Warfarin — Single doses of olanzapine did not affect the pharmacokinetics of warfarin [see Drug Interactions (7.1)].

Diazepam — Olanzapine did not influence the pharmacokinetics of diazepam or its active metabolite N-desmethyldiazepam. However, diazepam co-administered with olanzapine increased the orthostatic hypotension observed with either drug given alone [see Drug Interactions (7.1)].

Alcohol — Multiple doses of olanzapine did not influence the kinetics of ethanol [see Drug Interactions (7.1)].

Biperiden — Multiple doses of olanzapine did not influence the kinetics of biperiden.

Theophylline — Multiple doses of olanzapine did not affect the pharmacokinetics of theophylline or its metabolites.

8 USE IN SPECIFIC POPULATIONS

8.1 Pregnancy

Pregnancy Exposure Registry

There is a pregnancy exposure registry that monitors pregnancy outcomes in women exposed to atypical antipsychotics, including ZYPREXA RELPREVV, during pregnancy. Healthcare providers are encouraged to register patients by contacting the National Pregnancy Registry for Atypical Antipsychotics at 1-866-961-2388 or visit http://womensmentalhealth.org/clinical-and-research-programs/pregnancyregistry/.

Risk Summary

Neonates exposed to antipsychotic drugs, including ZYPREXA RELPREVV, during the third trimester are at risk for extrapyramidal and/or withdrawal symptoms following delivery (see Clinical Considerations). Overall available data from published epidemiologic studies of pregnant women exposed to olanzapine have not established a drug-associated risk of major birth defects, miscarriage, or adverse maternal or fetal outcomes (see Data). There are risks to the mother associated with untreated schizophrenia or bipolar I disorder and with exposure to antipsychotics, including ZYPREXA RELPREVV, during pregnancy (see Clinical Considerations).

Olanzapine was not teratogenic when administered orally to pregnant rats and rabbits at doses that are 9- and 30-times the daily oral maximum recommended human dose (MRHD), based on mg/m^2 body surface area; some fetal toxicities were observed at these doses (see Data).

The estimated background risk of major birth defects and miscarriage for the indicated populations is unknown. All pregnancies have a background risk of birth defects, loss, or other adverse outcomes. In the U.S. general population, the estimated background risk of major birth defects and miscarriage in clinically recognized pregnancies is 2% to 4% and 15% to 20%, respectively.

Clinical Considerations

Disease-associated maternal and embryo/fetal risk

There is a risk to the mother from untreated schizophrenia or bipolar I disorder, including increased risk of relapse, hospitalization, and suicide. Schizophrenia and bipolar I disorder are associated with increased adverse perinatal outcomes, including preterm birth. It is not known if this is a direct result of the illness or other comorbid factors.

Fetal/Neonatal adverse reactions

Extrapyramidal and/or withdrawal symptoms, including agitation, hypertonia, hypotonia, tremor, somnolence, respiratory distress, and feeding disorder have been reported in neonates who were exposed to antipsychotic drugs, including ZYPREXA RELPREVV, during the third trimester of pregnancy. These symptoms have varied in severity. Monitor neonates for extrapyramidal and/or withdrawal symptoms and manage symptoms appropriately. Some neonates recovered within hours or days without specific treatment; others required prolonged hospitalization.

Data

Human Data

Placental passage has been reported in published study reports; however, the placental passage ratio was highly variable ranging between 7% to 167% at birth following exposure during pregnancy. The clinical relevance of this finding is unknown.

Published data from observational studies, birth registries, case reports and meta-analyses that have evaluated the use of atypical antipsychotics during pregnancy do not establish an increased risk of major birth defects. A retrospective cohort study from a Medicaid database of 9258 women exposed to antipsychotics during pregnancy did not indicate an overall increased risk for major birth defects.

Animal Data

In oral reproduction studies in rats at doses up to 18 mg/kg/day and in rabbits at doses up to 30 mg/kg/day (9 and 30 times the daily oral MRHD based on mg/m^2 body surface area, respectively), no evidence of teratogenicity was observed. In an oral rat teratology study, early resorptions and increased numbers of nonviable fetuses were observed at a dose of 18 mg/kg/day (9 times the daily oral MRHD based on mg/m^2 body surface area), and gestation was prolonged at 10 mg/kg/day (5 times the daily oral MRHD based on mg/m^2 body surface area). In an oral rabbit teratology study, fetal toxicity manifested as increased resorptions and decreased fetal weight, occurred at a maternally toxic dose of 30 mg/kg/day (30 times the daily oral MRHD based on mg/m^2 body surface area). No evidence of teratogenicity or embryo-fetal toxicity was observed in rats or rabbits with olanzapine at intramuscular doses up to 75 mg/kg (1 and 2 times the MRHD of 300 mg every 2 weeks, respectively, based on mg/m^2 body surface area).

8.2 Lactation

Risk Summary

Olanzapine pamoate is present in human milk. There are reports of excess sedation, irritability, poor feeding, and extrapyramidal symptoms (tremors and abnormal muscle movements) in infants exposed to olanzapine pamoate through breast milk (see Clinical Considerations). There is no information on the effects of olanzapine pamoate on milk production.

The developmental and health benefits of breastfeeding should be considered along with the mother's clinical need for ZYPREXA RELPREVV and any potential adverse effects on the breastfed child from ZYPREXA RELPREVV or from the mother's underlying condition.

Clinical Considerations

Infants exposed to ZYPREXA RELPREVV should be monitored for excess sedation, irritability, poor feeding, and extrapyramidal symptoms (tremors and abnormal muscle movements).

8.3 Females and Males of Reproductive Potential

Infertility

Females

Based on the pharmacologic action of olanzapine (D2 receptor antagonism), treatment with ZYPREXA RELPREVV may result in an increase in serum prolactin levels, which may lead to a reversible reduction in fertility in females of reproductive potential [see Warnings and Precautions (5.17)].

8.4 Pediatric Use

Safety and effectiveness of ZYPREXA RELPREVV in children and adolescent patients have not been established [see Warnings and Precautions (5.7)].

Compared to patients from adult clinical trials, adolescents treated with oral ZYPREXA were likely to gain more weight, experience increased sedation, and have greater increases in total cholesterol, triglycerides, LDL cholesterol, prolactin and hepatic aminotransferase levels.

8.5 Geriatric Use

Clinical studies of ZYPREXA RELPREVV did not include sufficient numbers of subjects aged 65 and over to determine whether they respond differently from younger subjects. In the premarketing clinical studies with oral olanzapine, there was no indication of any different tolerability of olanzapine in elderly patients compared to younger patients with schizophrenia. Oral olanzapine studies in elderly patients with dementia-related psychosis have suggested that there may be a different tolerability profile in this population compared to younger patients with schizophrenia. Elderly patients with dementia-related psychosis treated with olanzapine are at an increased risk of death compared to placebo. In placebo-controlled studies of olanzapine in elderly patients with dementia-related psychosis, there was a higher incidence of cerebrovascular adverse events (e.g., stroke, transient ischemic attack) in patients treated with olanzapine compared to patients treated with placebo. In 5 placebo-controlled studies of olanzapine in elderly patients with dementia-related psychosis (n=1184), the following adverse reactions were reported in olanzapine-treated patients at an incidence of at least 2% and significantly greater than placebo-treated patients: falls, somnolence, peripheral edema, abnormal gait, urinary incontinence, lethargy, increased weight, asthenia, pyrexia, pneumonia, dry mouth and visual hallucinations. The rate of discontinuation due to adverse reactions was greater with olanzapine than placebo (13% vs 7%). Elderly patients with dementia-related psychosis treated with olanzapine are at an increased risk of death compared to placebo. Olanzapine is not approved for the treatment of patients with dementia-related psychosis [see Boxed Warning, Warnings and Precautions (5.3), and Patient Counseling Information (17)]. Olanzapine is not approved for the treatment of patients with dementia-related psychosis. Also, the presence of factors that might decrease pharmacokinetic clearance or increase the pharmacodynamic response to olanzapine should lead to consideration of a lower starting dose for any geriatric patient [see Boxed Warning, Dosage and Administration (2.1), and Warnings and Precautions (5.3)].

9 DRUG ABUSE AND DEPENDENCE

9.3 Dependence

In studies prospectively designed to assess abuse and dependence potential, olanzapine was shown to have acute depressive CNS effects but little or no potential of abuse or physical dependence in rats administered oral doses up to 15 times the daily oral MRHD (20 mg) and rhesus monkeys administered oral doses up to 8 times the daily oral MRHD based on mg/m^2 body surface area.

Olanzapine has not been systematically studied in humans for its potential for abuse, tolerance, or physical dependence. Because ZYPREXA RELPREVV is to be administered by healthcare professionals, the potential for misuse or abuse by patients is low.

10 OVERDOSAGE

10.1 Human Experience

During premarketing clinical studies of ZYPREXA RELPREVV, adverse reactions that presented with signs and symptoms consistent with olanzapine overdose, in particular, sedation (including coma) and/or delirium, were reported in patients following an injection of ZYPREXA RELPREVV [see Boxed Warning and Dosage and Administration (2.1)]. These reactions occurred in <0.1% of injections and in approximately 2% of patients who received injections for up to 46 months. These reactions were correlated with an unintentional rapid increase in serum olanzapine concentrations to supra-therapeutic ranges in some cases. While a rapid and greater than expected increase in serum olanzapine concentration has been observed in some patients with these reactions, the exact mechanism by which the drug was unintentionally introduced into the blood stream is not known. Clinical signs and symptoms included dizziness, confusion, disorientation, slurred speech, altered gait, difficulty ambulating, weakness, agitation, extrapyramidal symptoms, hypertension, convulsion, and reduced level of consciousness ranging from mild sedation to coma. Time after injection to event ranged from soon after injection to greater than 3 hours after injection. The majority of patients were hospitalized and some required supportive care, including intubation, in several cases. All patients had largely recovered by 72 hours. The risk of an event is the same at each injection, so the risk per patient is cumulative (i.e., increases with the number of injections) [see Warnings and Precautions (5.1)].

In postmarketing reports of overdose with oral olanzapine alone, symptoms have been reported in the majority of cases. In symptomatic patients, symptoms with ≥10% incidence included agitation/aggressiveness, dysarthria, tachycardia, various extrapyramidal symptoms, and reduced level of consciousness ranging from sedation to coma. Among less commonly reported symptoms were the following potentially medically serious reactions: aspiration, cardiopulmonary arrest, cardiac arrhythmias (such as supraventricular tachycardia and 1 patient experiencing sinus pause with spontaneous resumption of normal rhythm), delirium, possible neuroleptic malignant syndrome, respiratory depression/arrest, convulsion, hypertension, and hypotension. Eli Lilly and Company has received reports of fatality in association with overdose of oral olanzapine alone. In 1 case of death, the amount of acutely ingested oral olanzapine was reported to be possibly as low as 450 mg of oral olanzapine; however, in another case, a patient was reported to survive an acute olanzapine ingestion of approximately 2 g of oral olanzapine.

10.2 Management of Overdose

Post-injection delirium/sedation syndrome may occur with each injection of ZYPREXA RELPREVV. Signs and symptoms consistent with olanzapine overdose have been observed, and access to emergency response services must be readily available for safe use [see Boxed Warning and Warnings and Precautions (5.1)].

There is no specific antidote to olanzapine. Therefore, appropriate supportive measures should be initiated. Hypotension and circulatory collapse should be treated with appropriate measures such as intravenous fluids and/or sympathomimetic agents. (Do not use epinephrine, dopamine, or other sympathomimetics with beta-agonist activity, since beta stimulation may worsen hypotension in the setting of olanzapine-induced alpha blockade.) Respiratory support, including ventilation, may be required. Close medical supervision and monitoring should continue until the patient recovers.

The possibility of multiple drug involvement should be considered. In case of acute overdosage, establish and maintain an airway and ensure adequate oxygenation and ventilation, which may include intubation. The possibility of obtundation, seizures, or dystonic reaction of the head and neck following overdose may create a risk of aspiration with induced emesis. Cardiovascular monitoring should commence immediately and should include continuous electrocardiographic monitoring to detect possible arrhythmias.

11 DESCRIPTION

ZYPREXA RELPREVV is an atypical antipsychotic that belongs to the thienobenzodiazepine class. The chemical designation is 10H-thieno[2,3-b][1,5]benzodiazepine, 2-methyl-4-(4-methyl-1-piperazinyl)-,4,4′-methylenebis[3-hydroxy-2-naphthalenecarboxylate] (1:1), monohydrate. The formula is C17H22N4S•C23H14O6•H2O, which corresponds to a molecular weight of 718.8. The chemical structure is:

ZYPREXA RELPREVV is a long-acting form of olanzapine and is intended for deep intramuscular gluteal injection only.

ZYPREXA RELPREVV includes a single-dose vial of the drug product and a vial of the sterile diluent for ZYPREXA RELPREVV.

The drug product is olanzapine pamoate monohydrate, present as a yellow solid in a glass vial equivalent to 210, 300, or 405 mg olanzapine base per vial. The diluent for ZYPREXA RELPREVV is a clear, colorless to slightly yellow solution in a glass vial and is composed of carboxymethylcellulose sodium, mannitol, polysorbate 80, sodium hydroxide and/or hydrochloric acid for pH adjustment, and water for injection. The drug product is suspended in the diluent for ZYPREXA RELPREVV to a target concentration of 150 mg olanzapine per mL prior to intramuscular injection.

12 CLINICAL PHARMACOLOGY

12.1 Mechanism of Action

The mechanism of action of olanzapine, in the listed indications is unclear. However, the efficacy of olanzapine in schizophrenia could be mediated through a combination of dopamine and serotonin type 2 (5HT2) antagonism.

12.2 Pharmacodynamics

Olanzapine binds with high affinity to the following receptors: serotonin 5HT2A/2C, 5HT6 (Ki=4, 11, and 5 nM, respectively), dopamine D1-4 (Ki=11-31 nM), histamine H1 (Ki=7 nM), and adrenergic α1 receptors (Ki=19 nM). Olanzapine is an antagonist with moderate affinity binding for serotonin 5HT3 (Ki=57 nM) and muscarinic M1-5 (Ki=73, 96, 132, 32, and 48 nM, respectively). Olanzapine binds with low affinity to GABAA, BZD, and β-adrenergic receptors (Ki>10 μM).

12.3 Pharmacokinetics

The fundamental pharmacokinetic properties of olanzapine are similar for ZYPREXA RELPREVV and orally administered olanzapine. Refer to the section below describing the pharmacokinetics of orally administered olanzapine for details.

Slow dissolution of ZYPREXA RELPREVV, a practically insoluble salt, after a deep intramuscular gluteal injection of a dose of ZYPREXA RELPREVV results in prolonged systemic olanzapine plasma concentrations that are sustained over a period of weeks to months. An injection every 2 or 4 weeks provides olanzapine plasma concentrations that are similar to those achieved by daily doses of oral olanzapine. The steady-state plasma concentrations for ZYPREXA RELPREVV for doses of 150 mg to 405 mg every 2 or 4 weeks are within the range of steady-state olanzapine plasma concentration known to have been associated with oral doses of 5 mg to 20 mg olanzapine once daily. The change to a slow release, rate-controlled absorption process is the only fundamental pharmacokinetic difference between the administration of ZYPREXA RELPREVV and orally administered olanzapine. The effective half-life for olanzapine after intramuscular ZYPREXA RELPREVV administration is approximately 30 days as compared to a half-life after oral administration of approximately 30 hours. Exposure to olanzapine may persist for a period of months after a ZYPREXA RELPREVV injection. The long persistence of systemic concentrations of olanzapine may be an important consideration for the long-term clinical management of the patient. Typical systemic olanzapine plasma concentrations reach a peak within the first week after injection and are at trough level immediately prior to the next injection. The olanzapine plasma concentration fluctuation between the peak and trough is comparable to the peak and trough fluctuations associated with once daily oral dosing.

Dose Proportionality and Oral Dose Correspondence — ZYPREXA RELPREVV provides a dose of 150, 210, 300, or 405 mg olanzapine. An injection of a larger dose produces a dose-proportional increase in the systemic exposure. The olanzapine exposure after doses of ZYPREXA RELPREVV corresponds to exposure for oral doses of olanzapine. A ZYPREXA RELPREVV dose of 300 mg olanzapine injected every two weeks delivers approximately 20 mg olanzapine per day and a ZYPREXA RELPREVV dose of 150 mg olanzapine injected every two weeks delivers approximately 10 mg per day. These ZYPREXA RELPREVV doses sustain steady-state olanzapine concentrations over long periods of treatment.

Pharmacokinetic Impact of Switching to ZYPREXA RELPREVV from Oral Olanzapine — The switch from oral olanzapine to ZYPREXA RELPREVV changes the pharmacokinetics from an elimination-rate-controlled to an absorption-rate-controlled process. The switch to ZYPREXA RELPREVV may require treatment for a period of approximately 3 months to re-establish steady-state conditions. Initial treatment with ZYPREXA RELPREVV is recommended at a dose corresponding to the mg/day oral dose [see Dosage and Administration (2.1)]. Plasma concentrations of olanzapine during the first injection interval may be lower than those maintained by a corresponding oral dose. Even though the concentrations are lower, the olanzapine concentrations remained within a therapeutically effective range and supplementation with orally administered olanzapine was generally not necessary in clinical trials.

Olanzapine is extensively distributed throughout the body, with a volume of distribution of approximately 1000 L. It is 93% bound to plasma proteins over the concentration range of 7 to 1100 ng/mL, binding primarily to albumin and α1-acid glycoprotein.

Metabolism and Elimination — Following a single oral dose of ^14C labeled olanzapine, 7% of the dose of olanzapine was recovered in the urine as unchanged drug, indicating that olanzapine is highly metabolized. Approximately 57% and 30% of the dose was recovered in the urine and feces, respectively. In the plasma, olanzapine accounted for only 12% of the AUC for total radioactivity, indicating significant exposure to metabolites. After multiple dosing, the major circulating metabolites were the 10-N-glucuronide, present at steady state at 44% of the concentration of olanzapine, and 4′-N-desmethyl olanzapine, present at steady state at 31% of the concentration of olanzapine. Both metabolites lack pharmacological activity at the concentrations observed.

Direct glucuronidation and cytochrome P450 (CYP) mediated oxidation are the primary metabolic pathways for olanzapine. In vitro studies suggest that CYPs 1A2 and 2D6, and the flavin-containing monooxygenase system are involved in olanzapine oxidation. CYP2D6 mediated oxidation appears to be a minor metabolic pathway in vivo, because the clearance of olanzapine is not reduced in subjects who are deficient in this enzyme.

Intramuscular Formulations — There are two formulations of ZYPREXA which are available for intramuscular injection. One form (ZYPREXA RELPREVV) is described in this package insert. The other formulation (ZYPREXA IntraMuscular) is a solution of olanzapine. When ZYPREXA IntraMuscular is injected intramuscularly, olanzapine (as the free base) is rapidly absorbed and peak plasma concentrations occur within 15 to 45 minutes. With the exception of higher maximum plasma concentrations, the pharmacokinetics of olanzapine after ZYPREXA IntraMuscular are similar to those for orally administered olanzapine. Refer to the package insert for ZYPREXA IntraMuscular for additional information.

Specific Populations — In general, the decision to use ZYPREXA RELPREVV in specific populations should be thoughtfully considered. For patients who have never taken oral olanzapine, tolerability should be established with oral olanzapine prior to initiating treatment with ZYPREXA RELPREVV. The recommended starting dose is ZYPREXA RELPREVV 150 mg/4 wks, in patients who are debilitated, who have a predisposition to hypotensive reactions, who otherwise exhibit a combination of factors that may result in slower metabolism of olanzapine (e.g., nonsmoking female patients >65 years of age), or who may be more pharmacodynamically sensitive to olanzapine. When indicated, dose escalation should be performed with caution in these patients [see Dosage and Administration (2.1)]. Precautions noted below need to be carefully weighed.

Renal Impairment — Because olanzapine is highly metabolized before excretion and only 7% of the drug is excreted unchanged, renal dysfunction alone is unlikely to have a major impact on the pharmacokinetics of olanzapine. The pharmacokinetic characteristics of orally administered olanzapine were similar in patients with severe renal impairment and normal subjects, indicating that dosage adjustment based upon the degree of renal impairment is not required. In addition, olanzapine is not removed by dialysis. The effect of renal impairment on metabolite elimination has not been studied.

Hepatic Impairment — Although the presence of hepatic impairment may be expected to reduce the clearance of olanzapine, a study of the effect of impaired liver function in subjects (n=6) with clinically significant (Childs Pugh Classification A and B) cirrhosis revealed little effect on the pharmacokinetics of orally administered olanzapine.

Geriatric — In a study involving 24 healthy subjects, the mean elimination half-life of orally administered olanzapine was about 1.5 times greater in elderly (≥65 years) than in nonelderly subjects (<65 years). Caution should be used in dosing the elderly, especially if there are other factors that might additively influence drug metabolism and/or pharmacodynamic sensitivity [see Dosage and Administration (2.1)].

Gender — For both oral ZYPREXA and ZYPREXA RELPREVV higher average plasma concentrations of olanzapine were observed in women than in men. There were, however, no apparent differences between men and women in effectiveness or adverse effects. Dosage modifications based on gender should not be needed.

Smoking Status — For both oral ZYPREXA and ZYPREXA RELPREVV, studies have demonstrated that the clearance of olanzapine is higher in smokers than in nonsmokers, although dosage modifications are not routinely recommended.

Race — In vivo studies of orally administered olanzapine have shown that exposures are similar among Japanese, Chinese and Caucasians, especially after normalization for body weight differences. Dosage modifications for race are, therefore, not recommended.

Combined Effects — The combined effects of age, smoking, and gender could lead to substantial pharmacokinetic differences in populations. The clearance in young smoking males, for example, may be 3 times higher than that in elderly nonsmoking females. Dosing modification may be necessary in patients who exhibit a combination of factors that may result in slower metabolism of olanzapine [see Dosage and Administration (2.1)].

13 NONCLINICAL TOXICOLOGY

13.1 Carcinogenesis, Mutagenesis, Impairment of Fertility

Carcinogenesis — Oral carcinogenicity studies were conducted in mice and rats. Olanzapine was administered to mice in two 78-week studies at doses of 3, 10, 30/20 mg/kg/day (equivalent to 0.8-5 times the daily oral MRHD based on mg/m^2 body surface area) and 0.25, 2, 8 mg/kg/day (equivalent to 0.06-2 times the daily oral MRHD based on mg/m^2 body surface area). Rats were dosed for 2 years at doses of 0.25, 1, 2.5, 4 mg/kg/day (males) and 0.25, 1, 4, 8 mg/kg/day (females) (equivalent to 0.13-2 and 0.13-4 times the daily oral MRHD based on mg/m^2 body surface area, respectively). The incidence of liver hemangiomas and hemangiosarcomas was significantly increased in 1 mouse study in female mice at 2 times the daily oral MRHD based on mg/m^2 body surface area. These tumors were not increased in another mouse study in females dosed up to 2-5 times the daily oral MRHD based on mg/m^2 body surface area; in this study, there was a high incidence of early mortalities in males of the 30/20 mg/kg/day group. The incidence of mammary gland adenomas and adenocarcinomas was significantly increased in female mice dosed at ≥2 mg/kg/day and in female rats dosed at ≥4 mg/kg/day (0.5 and 2 times the daily oral MRHD based on mg/m^2 body surface area, respectively). Rats were also treated intramuscularly with ZYPREXA RELPREVV once a month for 2 years at doses of 5, 10, 20 mg/kg (males) and 10, 25, 50 mg/kg (females) (equivalent to 0.08-0.8 times the daily oral MRHD of 300 mg every 2 weeks based on mg/m^2 body surface area; dosing was limited due to local reactions at the IM injection site). The incidence of tumors in this study was not altered when compared to solution for ZYPREXA RELPREVV control or pamoic acid treated animals. Antipsychotic drugs have been shown to chronically elevate prolactin levels in rodents. Serum prolactin levels were not measured during the olanzapine carcinogenicity studies; however, measurements during subchronic toxicity studies showed that olanzapine elevated serum prolactin levels up to 4-fold in rats at the same doses used in the carcinogenicity study. An increase in mammary gland neoplasms has been found in rodents after chronic administration of other antipsychotic drugs and is considered to be prolactin mediated. The relevance for human risk of the finding of prolactin mediated endocrine tumors in rodents is unknown [see Warnings and Precautions (5.17)].

Mutagenesis — No evidence of genotoxic potential for olanzapine was found in the Ames reverse mutation test, in vivo micronucleus test in mice, the chromosomal aberration test in Chinese hamster ovary cells, unscheduled DNA synthesis test in rat hepatocytes, induction of forward mutation test in mouse lymphoma cells, or in vivo sister chromatid exchange test in bone marrow of Chinese hamsters.

Impairment of Fertility — In an oral fertility and reproductive performance study in rats, male mating performance, but not fertility, was impaired at a dose of 22.4 mg/kg/day and female fertility was decreased at a dose of 3 mg/kg/day (11 and 1.5 times the daily oral MRHD based on mg/m^2 body surface area, respectively). Discontinuance of olanzapine treatment reversed the effects on male mating performance. In female rats, the precoital period was increased and the mating index reduced at 5 mg/kg/day (2.5 times the daily oral MRHD based on mg/m^2 body surface area). Diestrous was prolonged and estrous delayed at 1.1 mg/kg/day (0.6 times the daily oral MRHD based on mg/m^2 body surface area); therefore olanzapine may produce a delay in ovulation.

13.2 Animal Toxicology and/or Pharmacology

In animal studies with olanzapine, the principal hematologic findings were reversible peripheral cytopenias in individual dogs dosed at 10 mg/kg (17 times the daily oral MRHD based on mg/m^2 body surface area), dose-related decreases in lymphocytes and neutrophils in mice, and lymphopenia in rats. A few dogs treated with 10 mg/kg developed reversible neutropenia and/or reversible hemolytic anemia between 1 and 10 months of treatment. Dose-related decreases in lymphocytes and neutrophils were seen in mice given doses of 10 mg/kg (equal to 2 times the daily oral MRHD based on mg/m^2 body surface area) in studies of 3 months' duration. Nonspecific lymphopenia, consistent with decreased body weight gain, occurred in rats receiving 22.5 mg/kg (11 times the daily oral MRHD based on mg/m^2 body surface area) for 3 months or 16 mg/kg (8 times the daily oral MRHD based on mg/m^2 body surface area) for 6 or 12 months. No evidence of bone marrow cytotoxicity was found in any of the species examined. Bone marrows were normocellular or hypercellular, indicating that the reductions in circulating blood cells were probably due to peripheral (non-marrow) factors.

14 CLINICAL STUDIES

14.1 Schizophrenia

The short-term effectiveness of ZYPREXA RELPREVV was established in an 8-week, placebo-controlled trial in adult patients (n=404) who were experiencing psychotic symptoms and met DSM-IV or DSM-IV-TR criteria for schizophrenia. Patients were randomized to receive injections of ZYPREXA RELPREVV 210 mg every 2 weeks, ZYPREXA RELPREVV 405 mg every 4 weeks, ZYPREXA RELPREVV 300 mg every 2 weeks, or placebo every 2 weeks. Patients were discontinued from their previous antipsychotics and underwent a 2-7 day washout period. No oral antipsychotic supplementation was allowed throughout the trial. The primary efficacy measure was change from baseline to endpoint in total Positive and Negative Syndrome Scale (PANSS) score (mean baseline total PANSS score 101). Total PANSS scores showed statistically significant improvement from baseline to endpoint with each dose of ZYPREXA RELPREVV (210 mg every 2 weeks, 405 mg every 4 weeks, and 300 mg every 2 weeks) as compared to placebo. The effectiveness of ZYPREXA RELPREVV in the treatment of schizophrenia is further supported by the established effectiveness of the oral formulation of olanzapine.

A longer-term trial enrolled patients with schizophrenia (n=1065) who had remained stable for 4 to 8 weeks on open-label treatment with oral olanzapine (mean baseline total PANSS score 56) and were then randomized to continue their current oral olanzapine dose (10, 15, or 20 mg/day); or to ZYPREXA RELPREVV 150 mg every 2 weeks (405 mg every 4 weeks, 300 mg every 2 weeks, or 45 mg every 4 weeks). No oral antipsychotic supplementation was allowed throughout the trial. The primary efficacy measure was time to exacerbation of symptoms of schizophrenia defined in terms of increases in Brief Psychiatric Rating Scale (BPRS) positive symptoms or hospitalization. ZYPREXA RELPREVV doses of 150 mg every 2 weeks, 405 mg every 4 weeks, and 300 mg every 2 weeks were each statistically significantly superior to low dose ZYPREXA RELPREVV (45 mg every 4 weeks).

16 HOW SUPPLIED/STORAGE AND HANDLING

16.1 How Supplied

ZYPREXA RELPREVV convenience kit is supplied in single dose cartons. Each carton includes one vial of olanzapine pamoate monohydrate in dosage strengths that are equivalent to 210 mg olanzapine (483 mg olanzapine pamoate monohydrate), 300 mg olanzapine (690 mg olanzapine pamoate monohydrate), and 405 mg olanzapine (931 mg olanzapine pamoate monohydrate) per vial; one vial of approximately 3 mL of diluent for ZYPREXA RELPREVV used to suspend the drug product; one 3-mL syringe with pre-attached 19-gauge, 1.5-inch (38 mm) Hypodermic Needle-Pro needle with needle protection device; and two 19-gauge, 1.5-inch (38 mm) Hypodermic Needle-Pro needles with needle protection device.

Needle-Pro® is a registered trademark of Smiths Medical.

NDC 61269-660-20 — single-dose convenience kit: 210 mg vial (VL7635) with rust flip-off cap and 3-mL vial of sterile diluent (VL7622) with gray flip-off cap

NDC 61269-661-20 — single-dose convenience kit: 300 mg vial (VL7636) with olive flip-off cap and 3-mL vial of sterile diluent (VL7622) with gray flip-off cap

NDC 61269-662-20 — single-dose convenience kit: 405 mg vial (VL7637) with steel blue flip-off cap and 3-mL vial of sterile diluent (VL7622) with gray flip-off cap

16.2 Storage and Handling

ZYPREXA RELPREVV should be stored at room temperature not to exceed 30°C (86°F).

When the drug product is suspended in the solution for ZYPREXA RELPREVV, it may be held at room temperature for 24 hours. The vial should be agitated immediately prior to product withdrawal. Once the suspension is withdrawn into the syringe, it should be used immediately [see Dosage and Administration (2.2)].

17 PATIENT COUNSELING INFORMATION

Advise the patient to read the FDA-approved patient labeling (Medication Guide).

Patients should be advised of the following issues and asked to alert their prescriber if these occur while taking ZYPREXA RELPREVV. Patients should be advised to call their doctor if they do not think they are getting better or have concerns about their condition.

Post-Injection Delirium/Sedation Syndrome

During premarketing clinical studies, reactions that presented with signs and symptoms consistent with olanzapine overdose have been reported in patients following an injection of ZYPREXA RELPREVV. It is mandatory that patients be enrolled in the ZYPREXA RELPREVV Patient Care Program to receive ZYPREXA RELPREVV treatment. Patients should be advised of the risk of post-injection delirium/sedation syndrome each time they receive an injection [see Warnings and Precautions (5.1, 5.2)]. Patient and caregivers should be advised that after each ZYPREXA RELPREVV injection, patients must be observed at the healthcare facility for at least 3 hours and must be accompanied to their destination upon leaving the facility. The Medication Guide should be distributed each time patients receive an injection.

Elderly Patients with Dementia-Related Psychosis: Increased Mortality and Cerebrovascular Adverse Events (CVAE), Including Stroke

Patients and caregivers should be advised that elderly patients with dementia-related psychosis treated with antipsychotic drugs are at an increased risk of death. Patients and caregivers should be advised that elderly patients with dementia-related psychosis treated with ZYPREXA had a significantly higher incidence of cerebrovascular adverse events (e.g., stroke, transient ischemic attack) compared with placebo.

ZYPREXA RELPREVV is not approved for elderly patients with dementia-related psychosis [see Boxed Warning and Warnings and Precautions (5.3)].

Neuroleptic Malignant Syndrome (NMS)

Patients and caregivers should be counseled that a potentially fatal symptom complex sometimes referred to as NMS has been reported in association with administration of antipsychotic drugs, including ZYPREXA. Signs and symptoms of NMS include hyperpyrexia, muscle rigidity, altered mental status, and evidence of autonomic instability (irregular pulse or blood pressure, tachycardia, diaphoresis, and cardiac dysrhythmia) [see Warnings and Precautions (5.5)].

Drug Reaction with Eosinophilia and Systemic Symptoms (DRESS)

Patients should be advised to report to their health care provider at the earliest onset of any signs or symptoms that may be associated with drug reaction with eosinophilia and systemic symptoms (DRESS) [see Warnings and Precautions (5.6)].

Hyperglycemia and Diabetes Mellitus

Patients should be advised of the potential risk of hyperglycemia-related adverse reactions related to ZYPREXA RELPREVV. Patients should be monitored regularly for worsening of glucose control. Patients who have diabetes should follow their doctor's instructions about how often to check their blood sugar while taking ZYPREXA RELPREVV [see Warnings and Precautions (5.7)].

Dyslipidemia

Patients should be counseled that dyslipidemia has occurred during treatment with ZYPREXA RELPREVV. Patients should have their lipid profile monitored regularly [see Warnings and Precautions (5.7)].

Weight Gain

Patients should be counseled that weight gain has occurred during treatment with ZYPREXA RELPREVV. Patients should have their weight monitored regularly [see Warnings and Precautions (5.7)].

Orthostatic Hypotension

Patients should be advised of the risk of orthostatic hypotension, and in association with the use of concomitant drugs that may potentiate the orthostatic effect of ZYPREXA RELPREVV, e.g., diazepam or alcohol [see Warnings and Precautions (5.9) and Drug Interactions (7)]. Patients should be advised to change positions carefully to help prevent orthostatic hypotension, and to lie down if they feel dizzy or faint, until they feel better. Patients should be advised to call their doctor if they experience any of the following signs and symptoms associated with orthostatic hypotension: dizziness, fast or slow heartbeat, or fainting.

Potential for Cognitive and Motor Impairment

Because ZYPREXA RELPREVV has the potential to impair judgment, thinking, or motor skills, patients should be cautioned about operating hazardous machinery, including automobiles, until they are reasonably certain that ZYPREXA RELPREVV therapy does not affect them adversely. Additionally, due to the risk of post-injection delirium/sedation syndrome, patients should not drive or operate heavy machinery for the remainder of the day of each injection [see Dosage and Administration (2.1) and Warnings and Precautions (5.1, 5.14)].

Body Temperature Regulation

Patients should be advised regarding appropriate care in avoiding overheating and dehydration. Patients should be advised to call their doctor right away if they become severely ill and have some or all of these symptoms of dehydration: sweating too much or not at all, dry mouth, feeling very hot, feeling thirsty, not able to produce urine [see Warnings and Precautions (5.15)].

Concomitant Medication

Patients should be advised to inform their healthcare providers if they are taking, or plan to take, ZYPREXA or Symbyax® (olanzapine/fluoxetine combination). Patients should also be advised to inform their healthcare providers if they are taking, plan to take, or have stopped taking any prescription or over-the-counter drugs, including herbal supplements, since there is a potential for interactions [see Drug Interactions (7)].

Alcohol

Patients should be advised to avoid alcohol while taking ZYPREXA RELPREVV [see Drug Interactions (7.1)].

Use in Specific Populations

Pregnancy — Advise women to notify their healthcare provider if they become pregnant or intend to become pregnant during treatment with ZYPREXA RELPREVV. Advise patients that ZYPREXA RELPREVV may cause extrapyramidal and/or withdrawal symptoms (agitation, hypertonia, hypotonia, tremor, somnolence, respiratory distress, and feeding disorder) in a neonate. Advise patients that there is a pregnancy exposure registry that monitors pregnancy outcomes in women exposed to ZYPREXA RELPREVV during pregnancy [see Use in Specific Populations (8.1)].

Lactation — Advise breastfeeding women using ZYPREXA RELPREVV to monitor infants for excess sedation, irritability, poor feeding and extrapyramidal symptoms (tremors and abnormal muscle movements) and to seek medical care if they notice these signs [see Use in Specific Populations (8.2)].

Infertility — Advise females of reproductive potential that ZYPREXA RELPREVV may impair fertility due to an increase in serum prolactin levels. The effects on fertility are reversible [see Use in Specific Populations (8.3)].

Pediatric Use — Safety and effectiveness of ZYPREXA RELPREVV in patients under 18 years have not been established [see Use in Specific Populations (8.4)].

Distributed by: H2-Pharma, LLC
Montgomery, AL 36117, USA

Licensed by: CHEPLAPHARM Registration GmbH, Weiler Straße 5e, 79540 Lörrach, Germany

CHEPLAPHARM Registration GmbH under the license of CHEPLAPHARM Schweiz GmbH

Medication Guide

ZYPREXA® RELPREVV™ (zy-PREX-a REL-prev)

(olanzapine)

For Extended Release Injectable Suspension

Read the Medication Guide that comes with ZYPREXA RELPREVV before you start taking it and each time before you get an injection. There may be new information. This Medication Guide does not take the place of talking to your doctor about your medical condition or treatment. Talk with your doctor if there is something you do not understand or you want to learn more about ZYPREXA RELPREVV.

What is the most important information I should know about ZYPREXA RELPREVV?

Before you receive ZYPREXA RELPREVV treatment you must:

- understand the risks and benefits of ZYPREXA RELPREVV treatment. Your doctor will talk to you about the risks and benefits of ZYPREXA RELPREVV treatment.
- register in the ZYPREXA RELPREVV Patient Care Program. You must agree to the rules of the ZYPREXA RELPREVV Patient Care Program before you register.

ZYPREXA RELPREVV may cause serious side effects, including:

1. Post-injection Delirium Sedation Syndrome (PDSS).
2. Increased risk of death in elderly people who are confused, have memory loss and have lost touch with reality (dementia-related psychosis).
3. High blood sugar (hyperglycemia).
4. High fat levels in your blood (increased cholesterol and triglycerides), especially in teenagers age 13 to 17.
5. Weight gain, especially in teenagers age 13 to 17.

These serious side effects are described below.

1. Post-injection Delirium Sedation Syndrome (PDSS).PDSS is a serious problem that can happen after you get a ZYPREXA RELPREVV injection if the medicine gets in your blood too fast. This problem usually happens within 3 hours after you receive ZYPREXA RELPREVV. If the medicine gets in your blood too fast, you may have some of the following symptoms:
  - feel more sleepy than usual
  - feel dizzy
  - feel confused or disoriented
  - trouble talking or walking
  - muscles feel stiff or shaking
  - feel weak
  - feel grouchy or angry
  - feel nervous or anxious
  - higher blood pressure
  - seizures (convulsions)
  - pass out (become unconscious or coma)
  You will need to stay at the clinic where you receive the injection for at least 3 hours so your doctor can make sure you do not have symptoms of PDSS. When you leave the clinic someone must be with you. If you have symptoms of PDSS after you leave the clinic, get medical help or go to an emergency room right away.
2. Increased risk of death in elderly people who are confused, have memory loss and have lost touch with reality (dementia-related psychosis). ZYPREXA RELPREVV is not approved for treating psychosis in elderly people with dementia.
3. High blood sugar (hyperglycemia).High blood sugar can happen if you have diabetes already or if you have never had diabetes. High blood sugar could lead to:
  - a build up of acid in your blood due to ketones (ketoacidosis)
  - coma
  - death
  Your doctor should do tests to check your blood sugar before you start taking ZYPREXA RELPREVV and during treatment. In people who do not have diabetes, sometimes high blood sugar goes away when ZYPREXA RELPREVV is stopped. People with diabetes and some people who did not have diabetes before taking ZYPREXA RELPREVV need to take medicine for high blood sugar even after they stop taking ZYPREXA RELPREVV.
  If you have diabetes, follow your doctor's instructions about how often to check your blood sugar while taking ZYPREXA RELPREVV.
  Call your doctor if you have any of these symptoms of high blood sugar (hyperglycemia) while taking ZYPREXA RELPREVV:
  - feel very thirsty
  - need to urinate more than usual
  - feel very hungry
  - feel weak or tired
  - feel sick to your stomach
  - feel confused or your breath smells fruity
4. High fat levels in your blood (cholesterol and triglycerides). High fat levels may happen in people treated with ZYPREXA RELPREVV, especially in teenagers (13 to 17 years old). ZYPREXA RELPREVV is not approved in patients less than 18 years old. You may not have any symptoms, so your doctor should do blood tests to check your cholesterol and triglyceride levels before you start taking ZYPREXA RELPREVV and during treatment.
5. Weight gain. Weight gain is very common in people who take ZYPREXA RELPREVV. Teenagers (13 to 17 years old) are more likely to gain weight and to gain more weight than adults. ZYPREXA RELPREVV is not approved in patients less than 18 years old. Some people may gain a lot of weight while taking ZYPREXA RELPREVV, so you and your doctor should check your weight regularly. Talk to your doctor about ways to control weight gain, such as eating a healthy, balanced diet, and exercising.

What is ZYPREXA RELPREVV?

ZYPREXA RELPREVV is a long-acting prescription medicine given by injection and used to treat schizophrenia in adults. The symptoms of schizophrenia include:

- hearing voices
- seeing things that are not there
- having beliefs that are not true
- being suspicious or withdrawn

Some of your symptoms of schizophrenia may improve with treatment with ZYPREXA RELPREVV. If you do not think you are getting better, call your doctor.

It is not known if ZYPREXA RELPREVV is safe and effective in children under 18 years of age.

What should I tell my doctor before taking ZYPREXA RELPREVV?

ZYPREXA RELPREVV may not be right for you. Before starting ZYPREXA RELPREVV, tell your doctor if you have or had:

- heart problems
- seizures
- diabetes or high blood sugar levels (hyperglycemia)
- high cholesterol or triglyceride levels in your blood
- liver problems
- low or high blood pressure
- strokes or "mini-strokes" also called transient ischemic attacks (TIAs)
- Alzheimer's disease
- narrow-angle glaucoma
- enlarged prostate in men
- bowel obstruction
- breast cancer
- thoughts of suicide or hurting yourself
- any other medical condition
- are pregnant or plan to become pregnant. It is not known if ZYPREXA RELPREVV will harm your unborn baby.
  - If you become pregnant while receiving ZYPREXA, talk to your healthcare provider about registering with the National Pregnancy Registry for Atypical Antipsychotics. You can register by calling 1-866-961-2388 or go to http://womensmentalhealth.org/clinical-and-research-programs/pregnancyregistry/.
- are breast-feeding or plan to breast-feed. ZYPREXA RELPREVV passes into your breast milk. Talk to your doctor about the best way to feed your baby if you take ZYPREXA RELPREVV.

Tell your doctor if you exercise a lot or are in hot places often.

The symptoms of schizophrenia may include thoughts of suicide or of hurting yourself or others. If you have these thoughts at any time, tell your doctor or go to an emergency room right away.

Tell your doctor about all the medicines that you take, including prescription and nonprescription medicines, vitamins, and herbal supplements. ZYPREXA RELPREVV and some medicines may interact with each other and may not work as well, or cause possible serious side effects. Your doctor can tell you if it is safe to take ZYPREXA RELPREVV with your other medicines. Do not start or stop any medicine while taking ZYPREXA RELPREVV without talking to your doctor first.

How should I receive ZYPREXA RELPREVV?

- ZYPREXA RELPREVV will be injected into the muscle in your buttock (gluteus) by your doctor or nurse at the clinic.
- After receiving ZYPREXA RELPREVV, you will need to stay at the clinic for at least 3 hours.
- When you leave the clinic, someone must be with you.
- Call your doctor if you do not think you are getting better or have any concerns about your condition while taking ZYPREXA RELPREVV.

What should I avoid while receiving ZYPREXA RELPREVV?

- ZYPREXA RELPREVV can cause sleepiness and may affect your ability to make decisions, think clearly, or react quickly. Do not drive, operate heavy machinery, or do other dangerous activities until you know how ZYPREXA RELPREVV affects you. You should not drive or operate heavy machinery for the rest of the day after each injection.
- Avoid drinking alcohol while taking ZYPREXA RELPREVV. Drinking alcohol while you take ZYPREXA RELPREVV may make you sleepier than if you take ZYPREXA RELPREVV alone.

What are the possible side effects of ZYPREXA RELPREVV?

Serious side effects may happen when you take ZYPREXA RELPREVV, including:

- See "What is the most important information I should know about ZYPREXA RELPREVV?", which describes the risk of post-injection delirium sedation syndrome (PDSS), increased risk of death in elderly people with dementia-related psychosis and the risks of high blood sugar, high cholesterol and triglyceride levels, and weight gain.
- Increased incidence of stroke or "mini-strokes" called transient ischemic attacks (TIAs) in elderly people with dementia-related psychosis (elderly people who have lost touch with reality due to confusion and memory loss). ZYPREXA RELPREVV is not approved for these patients.
- Neuroleptic Malignant Syndrome (NMS):NMS is a rare but very serious condition that can happen in people who take antipsychotic medicines, including ZYPREXA RELPREVV. NMS can cause death and must be treated in a hospital. Call your doctor right away if you become severely ill and have any of these symptoms:
  - high fever
  - excessive sweating
  - rigid muscles
  - confusion
  - changes in your breathing, heartbeat, and blood pressure
- Drug Reaction with Eosinophilia and Systemic Symptoms (DRESS): DRESS can occur with ZYPREXA RELPREVV. Features of DRESS may include rash, fever, swollen glands and other internal organ involvement such as liver, kidney, lung and heart. DRESS is sometimes fatal; therefore, tell your doctor immediately if you experience any of these signs.
- Tardive Dyskinesia: This condition causes body movements that keep happening and that you can not control. These movements usually affect the face and tongue. Tardive dyskinesia may not go away, even if you stop taking ZYPREXA RELPREVV. It may also start after you stop taking ZYPREXA RELPREVV. Tell your doctor if you get any body movements that you can not control.
- Decreased blood pressure when you change positions, with symptoms of dizziness, fast or slow heartbeat, or fainting.
- Difficulty swallowing, that can cause food or liquid to get into your lungs.
- Seizures: Tell your doctor if you have a seizure during treatment with ZYPREXA RELPREVV.
- Problems with control of body temperature:You could become very hot, for instance when you exercise a lot or stay in an area that is very hot. It is important for you to drink water to avoid dehydration. Call your doctor right away if you become severely ill and have any of these symptoms of dehydration:
  - sweating too much or not at all
  - dry mouth
  - feeling very hot
  - feeling thirsty
  - not able to produce urine

Common side effects of ZYPREXA RELPREVV include: headache, sleepiness or drowsiness, weight gain, dry mouth, diarrhea, nausea, common cold, eating more (increased appetite), vomiting, cough, back pain, or pain at the injection site.

Tell your doctor about any side effect that bothers you or that does not go away.

These are not all the possible side effects with ZYPREXA RELPREVV. For more information, ask your doctor or pharmacist.

Call your doctor for medical advice about side effects. You may report side effects to FDA at 1-800-FDA-1088.

General information about ZYPREXA RELPREVV

Medicines are sometimes prescribed for purposes other than those listed in a Medication Guide.

This Medication Guide summarizes the most important information about ZYPREXA RELPREVV. If you would like more information, talk with your doctor. You can ask your doctor or pharmacist for information about ZYPREXA RELPREVV that was written for healthcare professionals. For more information about ZYPREXA RELPREVV call 1-866-770-9010.

What are the ingredients in ZYPREXA RELPREVV?

Active ingredient: olanzapine

Inactive ingredients: carboxymethylcellulose sodium, mannitol, polysorbate 80, sodium hydroxide and/or hydrochloric acid for pH adjustment, and water for injection

This Medication Guide has been approved by the U.S. Food and Drug Administration.

Medication Guide revised October, 2023

Distributed by: H2-Pharma, LLC
Montgomery, AL 36117, USA

Licensed by:
CHEPLAPHARM Registration GmbH
Weilerstr. 5e, 79540 Lörrach, Germany

CHEPLAPHARM Registration GmbH under the license of CHEPLAPHARM Schweiz GmbH

INSTRUCTIONS FOR USE

Instructions to Reconstitute and Administer Single-Dose vial of Zyprexa® Relprevv®
FOR DEEP INTRAMUSCULAR GLUTEAL INJECTION ONLY.
NOT TO BE INJECTED INTRAVENOUSLY OR SUBCUTANEOUSLY.
STEP 1
PREPARING MATERIALS
Convenience kit includes:
(see Figure 1 on right)
- Single-dose vial of Zyprexa Relprevv powder
- 3-mL vial of diluent
- One 3-mL syringe with pre-attached 19-gauge, 1.5-inch (38 mm) Hypodermic Needle-Pro® needle with needle protection device
- Two 19-gauge, 1.5-inch (38 mm) Hypodermic Needle-Pro needles with needle protection device
— For obese patients, a 2-inch (50 mm), 19-gauge or larger needle (not included in convenience kit) may be used for administration.
 | Zyprexa Relprevv must be suspended using only the diluent supplied in the convenience kit.
It is recommended that gloves are used when reconstituting, as Zyprexa Relprevv may be irritating to the skin. Flush with water if contact is made with skin.
STEP 2
DETERMINING RECONSTITUTION VOLUME
Refer to the table at right to determine the amount of diluent to be added to powder for reconstitution of each vial strength.
 | It is important to note that there is more diluent in the vial than is needed to reconstitute.
STEP 3
RECONSTITUTING ZYPREXA RELPREVV
Please read the Hypodermic Needle-Pro Instructions for Use before proceeding with Step 3. Failure to follow these instructions may result in a needle stick injury.
3.1 | Loosen the powder by lightly tapping the vial.
3.2 | Open the prepackaged Hypodermic Needle-Pro syringe and needle with needle protection device.
3.3 | Withdraw the pre-determined diluent volume (Step 2) into the syringe.
3.4 | Inject the diluent into the powder vial.
3.5 | Withdraw air to equalize the pressure in the vial by pulling back slightly on the plunger in the syringe.
3.6 | Remove the needle from the vial, holding the vial upright to prevent any loss of material.
3.7 | Engage the needle safety device (refer to complete Hypodermic Needle-Pro Instructions for Use).
3.8 | Pad a hard surface to cushion impact (see Figure 2). Tap the vial firmly and repeatedly on the surface until no powder is visible.
3.9 | Visually check the vial for clumps. Unsuspended powder appears as yellow, dry clumps clinging to the vial. Additional tapping may be required if large clumps remain (see Figure 3).
3.9 | Visually check the vial for clumps. Unsuspended powder appears as yellow, dry clumps clinging to the vial. Additional tapping may be required if large clumps remain (see Figure 3).
3.10 | Shake the vial vigorously until the suspension appears smooth and is consistent in color and texture. The suspended product will be yellow and opaque (see Figure 4).
If foam forms, let vial stand to allow foam to dissipate.
If the product is not used right away, it should be shaken vigorously to re-suspend. Reconstituted Zyprexa Relprevv remains stable at room temperature for up to 24 hours in the vial.
STEP 4
INJECTING ZYPREXA RELPREVV
 | IMPORTANT
Before administering the injection, confirm there will be someone to accompany the patient after the 3-hour observation period. If this cannot be confirmed, do not give the injection.
Refer to the table at right to determine the final volume to inject. Suspension concentration is 150 mg/mL Zyprexa Relprevv.
4.1 | Attach a new safety needle to the syringe.
4.2 | Slowly withdraw the desired amount into the syringe.
 | SOME EXCESS PRODUCT WILL REMAIN IN THE VIAL.
4.3 | Engage the needle safety device and remove the needle from syringe.
4.4 | For administration, select the 19-gauge, 1.5-inch (38 mm) Hypodermic Needle-Pro needle with needle protection device. For obese patients, a 2-inch (50 mm), 19-gauge or larger needle (not included in convenience kit) may be used. To help prevent clogging, a 19-gauge or larger needle must be used.
4.5 | Attach the new safety needle to the syringe prior to injection. Once the suspension has been removed from the vial, it should be injected immediately.
 | FOR DEEP INTRAMUSCULAR GLUTEAL INJECTION ONLY.
 | DO NOT INJECT INTRAVENOUSLY OR SUBCUTANEOUSLY.
4.6 | Select and prepare a site for injection in the gluteal area.
4.7 | After insertion of the needle into the muscle, aspirate for several seconds to ensure that no blood appears. If any blood is drawn into the syringe, discard the syringe and the dose and begin with a new convenience kit. The injection should be performed with steady, continuous pressure.
 | DO NOT MASSAGE THE INJECTION SITE.
4.8 | Engage the needle safety device.
4.9 | Dispose of the vials, needles, and syringe appropriately after injection. The vial is for single-dose only.
Zyprexa® Relprevv® is a registered trademark of CHEPLAPHARM.
CHEPLAPHARM Registration GmbH under the license of CHEPLAPHARM Schweiz GmbH
Literature revised: October, 2023
Smiths Medical
Jelco®
Hypodermic Needle-Pro® Needle
With Needle Protection Device
1. | DESCRIPTION:
 | The Hypodermic Needle-Pro® device is a sterile, single use device. It includes a needle and needle safety sheath. The Needle-Pro® device can be used with a Luer slip or Luer lock syringe.
2. | INDICATIONS FOR USE:
 | This device is intended for injection or aspiration of fluids. The needle protection device covers the needle after use to help prevent needle sticks.
3. | CONTRAINDICATIONS:
 | None known.
4. | WARNINGS:
4.1 | A needle stick with a contaminated needle may cause infectious diseases.
4.2 | Intentional disengagement of the Needle-Pro® device may result in a needle stick with a contaminated needle.
4.3 | Bent or damaged needles can result in breakage or damage to the tissue or accidental needle puncture. If the needle is bent or damaged, no attempt should be made to straighten the needle or engage the Needle-Pro® device. The Needle-Pro® device may not properly contain a bent needle and/or the needle could puncture the needle protection device which may result in a needle stick with a contaminated needle.
4.4 | Mishandling of the needle protection device may cause needles, especially short or small gauge needles, to bend whereby they protrude from the needle protector sheath which may result in a contaminated needle stick.
4.5 | Do not use with Paraldehyde.
5. | CAUTION:
5.1 | Do Not Reuse: Medical devices require specific material characteristics to perform as intended. These characteristics have been verified for single use only. Any attempt to re-process the device for subsequent re-use may adversely affect the integrity of the device or lead to deterioration in performance.
5.2 | Follow standard infection control procedures as specified by the Centers for Disease Control and Prevention (USA) or local equivalent.
6. | INSTRUCTIONS FOR USE:
6.1 | Peel blister pouch and remove device.
6.2 | Attach a syringe (if not already attached) to the Luer connection of the Needle-Pro® device with an easy twisting motion. Seat the needle firmly on the Needle-Pro® device with a push and a clockwise twist, then pull the needle cap straight away from the needle.
6.3 | After procedure is completed, press the needle into the sheath using a one-handed technique. Perform a one-handed technique by gently pressing the sheath against a flat surface. As The Sheath Is Pressed (Fig. 1), The Needle Is Firmly Engaged Into The Sheath (Fig. 2).
6.4 | Visually confirm that the needle is fully engaged into the needle protection sheath.
6.5 | Only remove the Needle-Pro® device with engaged needle from the syringe when required by a specific medical procedure. Remove by grasping the Luer hub of the needle protection device with thumb and forefinger, keeping the free fingers clear of the end of the device containing the needle point. (See Fig. 3)
6.6 | After use, place sharps in a suitable sharps container. Dispose of contaminated product in a safe manner according to Centers for Disease Control and Prevention, USA and Federal/State/Local regulations (EPA, OSHA) and health care facility guidelines or local equivalent.
 | NOTE: Additional dead space added by Needle-Pro® device averages 0.036 mL.
Needle-Pro; and the color orange applied to the needle protection device, Jelco design mark and Smiths Medical design mark are trademarks of Smiths Medical. The symbol ® indicates the trademark is registered in the U.S. Patent and Trademark Office and certain other countries.
© 2019 Smiths Medical. All rights reserved.
Caution • Do Not Reuse • Not made with natural rubber latex • Do not use if package is damaged • Sterilized using ethylene oxide • Non-pyrogenic fluid path • Caution: Federal (USA) law restricts this device to sale by or on the order of a physician • Catalogue Number • Batch Code • Date of Manufacture • Use by • Quantity • Manufacturer • Authorized Representative in the European Community • Keep dry • Keep away from sunlight
Manufacturer:
Smiths Medical ASD, Inc.
6000 Nathan Lane North
Minneapolis, MN 55442 USA
Tel: 1 800 258 5361 (US/CA)
Tel: +1 614 210 7300
www.smiths-medical.com
Rx ONLY
CE
2797
ZYPR-0002-SM10018196-002-IFU-20200204

PACKAGE LABEL - ZYPREXA Relprevv 210 mg

NDC 61269-660-20

ZYPREXA® Relprevv™

(olanzapine)

For Extended Release Injectable Suspension

210 mg/vial Single-Dose Vial Convenience Kit

Medication Guide is to be dispensed to patients.

VL7635/VL7622

Convenience kit includes:

Single-Dose vial of Zyprexa® Relprevv™ 210 mg/vial

One 3-mL vial of diluent

One 3-mL syringe with pre-attached 19-gauge, 1.5-inch Hypodermic Needle-Pro® needle with needle protection device

Two 19-gauge, 1.5-inch Hypodermic Needle-Pro needles with needle protection device

Hypodermic Needle-Pro is a registered trademark of Smiths Medical.

Reconstitute each vial with 1.3 mL of enclosed diluent. The resultant solution will contain 150 mg/mL.

Rx only

FOR DEEP INTRAMUSCULAR GLUTEAL INJECTION ONLY.

Dosing Frequency: Once every two weeks

CHEPLAPHARM

PACKAGE LABEL - ZYPREXA Relprevv 300 mg

NDC 61269-661-20

ZYPREXA® Relprevv™

(olanzapine)

For Extended Release Injectable Suspension

300 mg/vial Single-Dose Vial Convenience Kit

Medication Guide is to be dispensed to patients.

VL7636/VL7622

Convenience kit includes:

Single-Dose vial of Zyprexa® Relprevv™ 300 mg/vial

One 3-mL vial of diluent

One 3-mL syringe with pre-attached 19-gauge, 1.5-inch Hypodermic Needle-Pro® needle with needle protection device

Two 19-gauge, 1.5-inch Hypodermic Needle-Pro needles with needle protection device

Hypodermic Needle-Pro is a registered trademark of Smiths Medical.

Reconstitute each vial with 1.8 mL of enclosed diluent. The resultant solution will contain 150 mg/mL.

Rx only

FOR DEEP INTRAMUSCULAR GLUTEAL INJECTION ONLY.

Dosing Frequency: Once every two or four weeks

CHEPLPHARM

PACKAGE LABEL - ZYPREXA Relprevv 405 mg

NDC 61269-662-20

ZYPREXA® Relprevv™

(olanzapine)

For Extended Release Injectable Suspension

405 mg/vial Single-Dose Vial Convenience Kit

Medication Guide is to be dispensed to patients.

VL7637/VL7622

Convenience kit includes:

Single-Dose vial of Zyprexa® Relprevv™ 405 mg/vial

One 3-mL vial of diluent

One 3-mL syringe with pre-attached 19-gauge, 1.5-inch Hypodermic Needle-Pro® needle with needle protection device

Two 19-gauge, 1.5-inch Hypodermic Needle-Pro needles with needle protection device

Hypodermic Needle-Pro is a registered trademark of Smiths Medical.

Reconstitute each vial with 2.3 mL of enclosed diluent. The resultant solution will contain 150 mg/mL.

Rx only

FOR DEEP INTRAMUSCULAR GLUTEAL INJECTION ONLY.

Dosing Frequency: Once every four weeks

CHEPLAPHARM